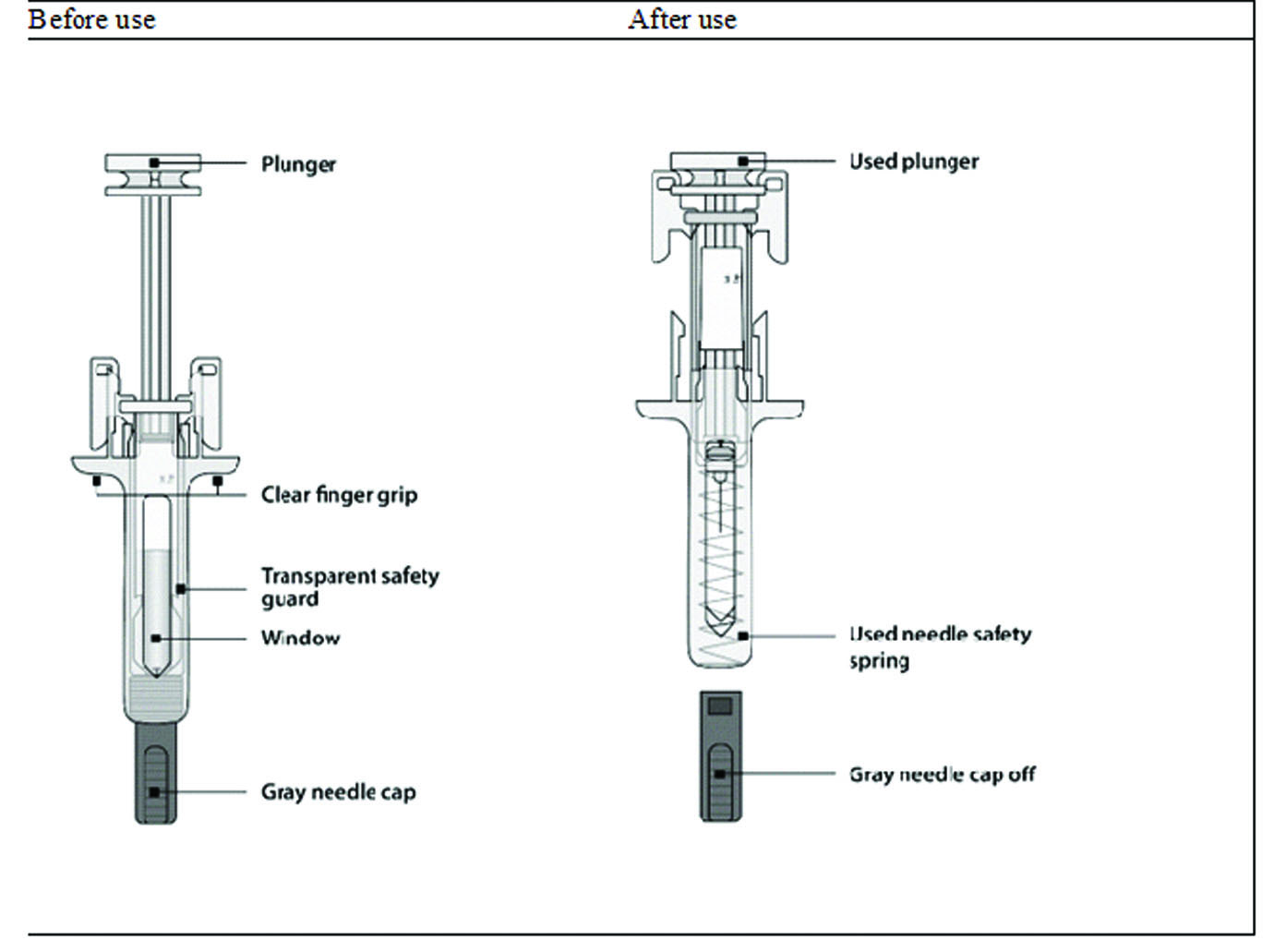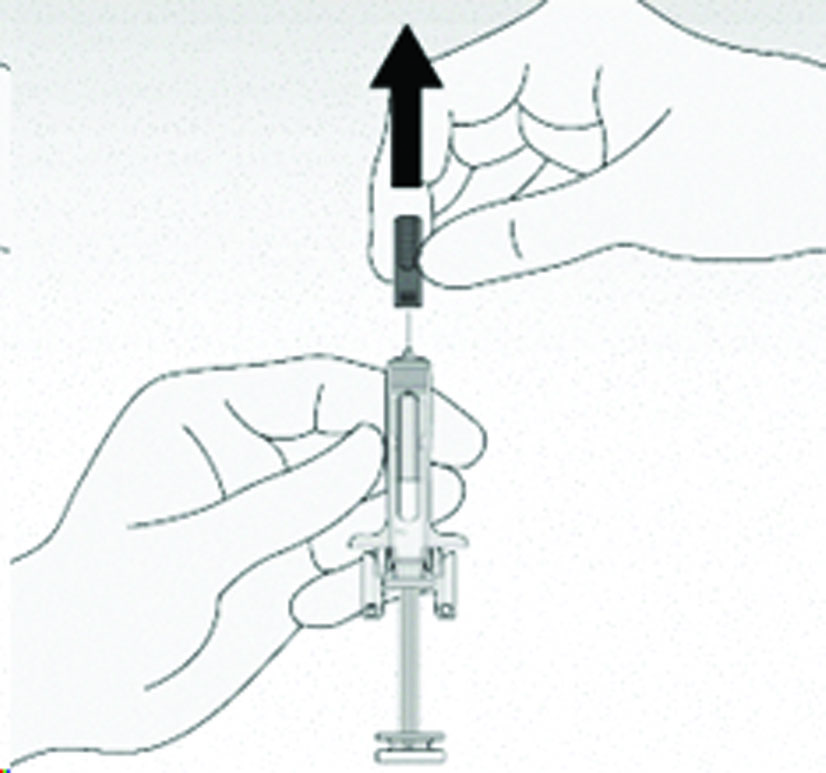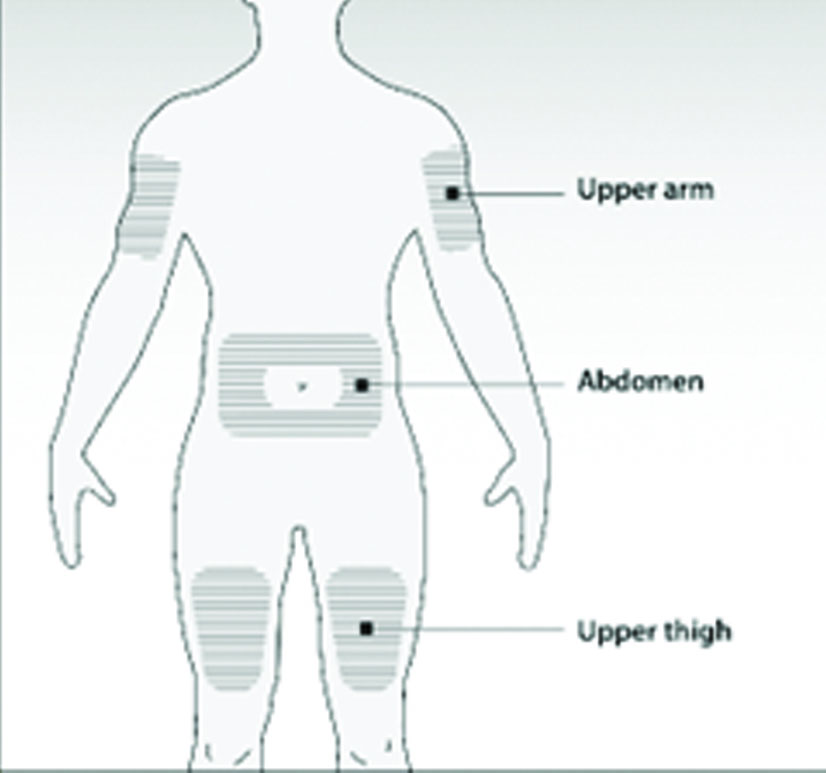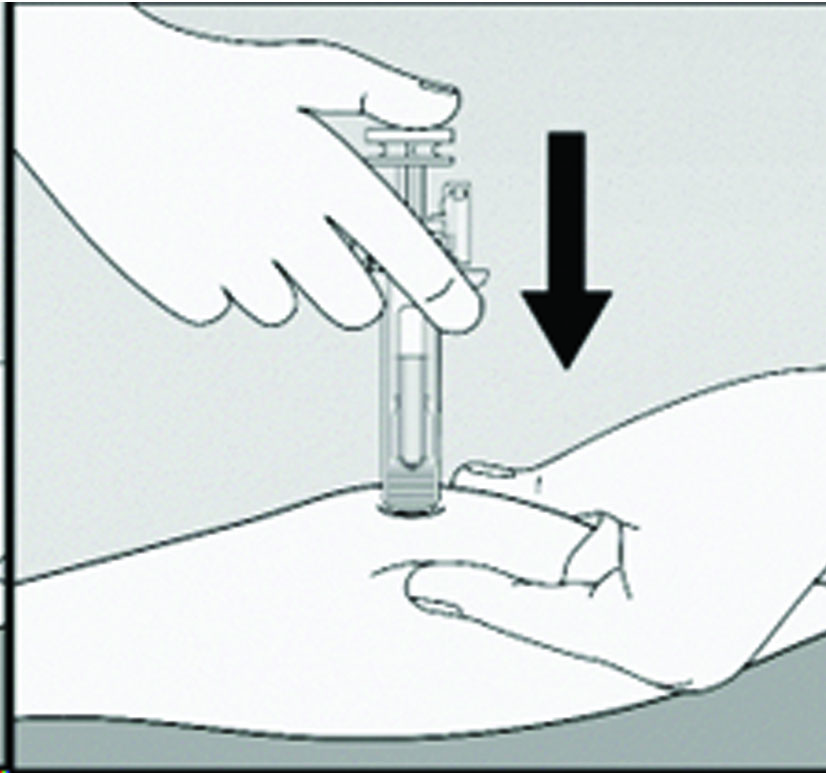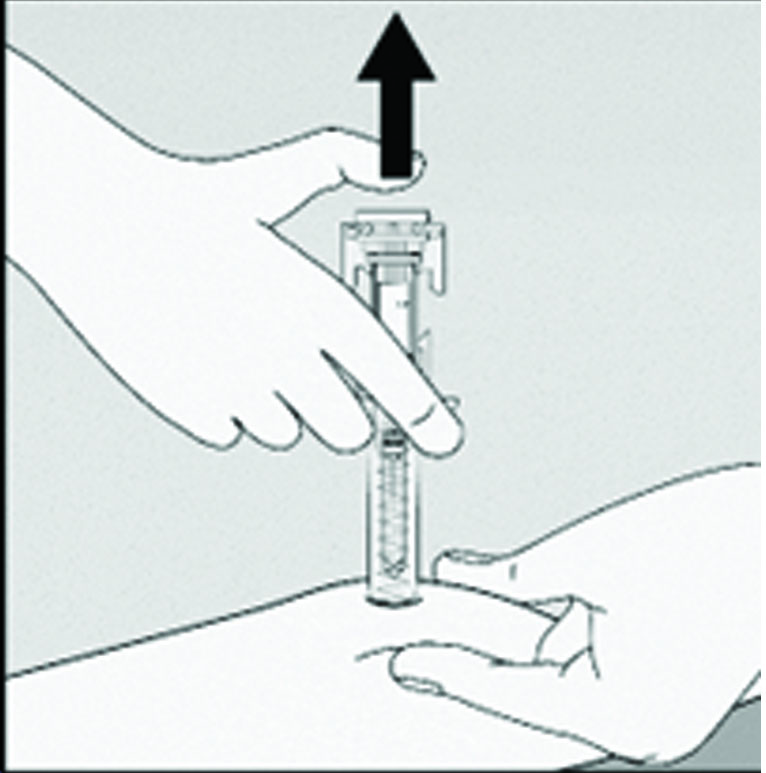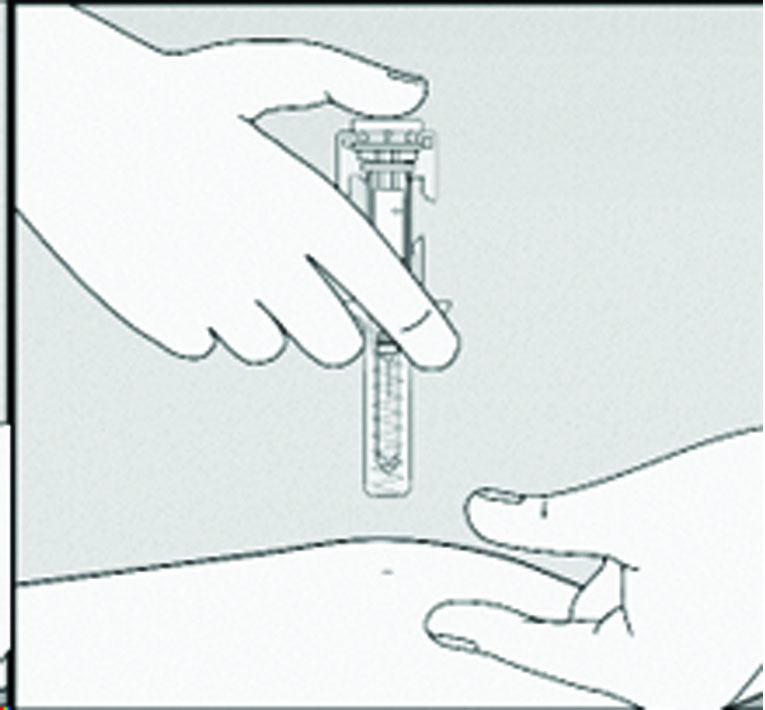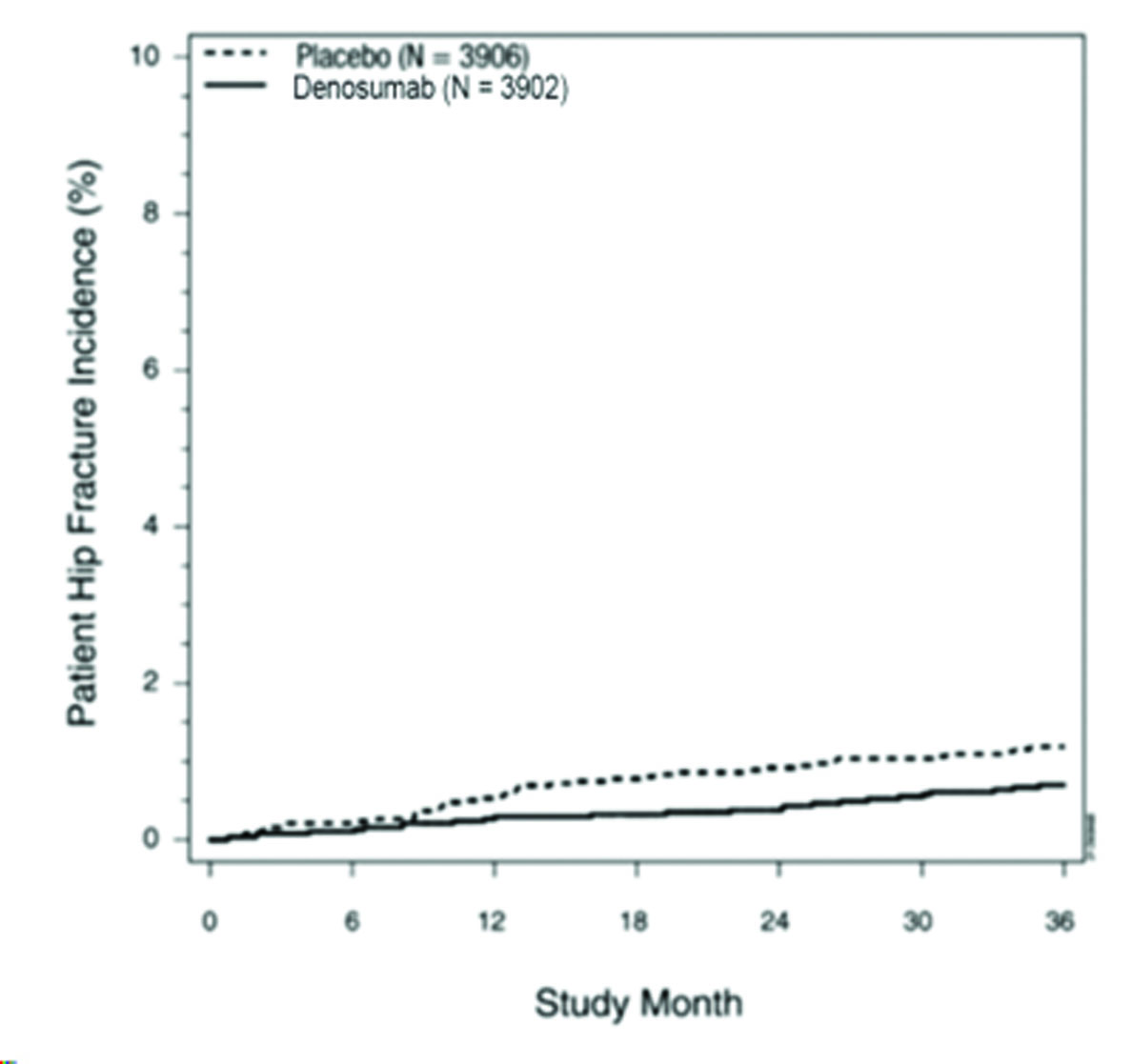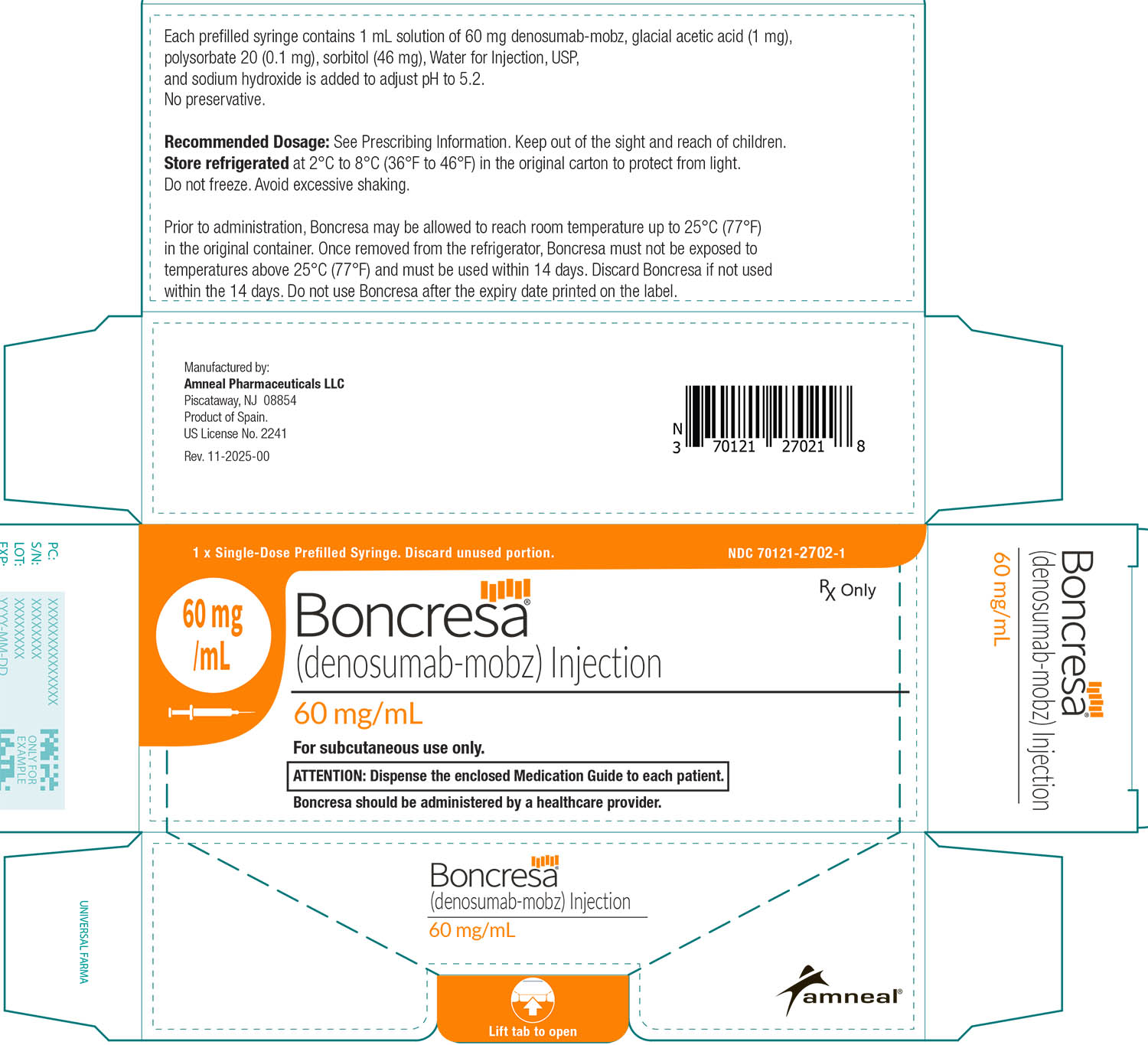 DRUG LABEL: Boncresa
NDC: 70121-2702 | Form: INJECTION, SOLUTION
Manufacturer: Amneal Pharmaceuticals LLC
Category: prescription | Type: HUMAN PRESCRIPTION DRUG LABEL
Date: 20251222

ACTIVE INGREDIENTS: DENOSUMAB 60 mg/1 mL
INACTIVE INGREDIENTS: SORBITOL; ACETIC ACID; POLYSORBATE 20; SODIUM HYDROXIDE; WATER

HIGHLIGHTS OF PRESCRIBING INFORMATION

These highlights do not include all the information needed to use BONCRESA safely and effectively. See full prescribing information for BONCRESA.
BONCRESA® (denosumab-mobz) injection, for subcutaneous use
Initial U.S. Approval: 2010
BONCRESA (denosumab-mobz) is biosimilar* to PROLIA® (denosumab)

WARNING: SEVERE HYPOCALCEMIA IN PATIENTS WITH ADVANCED KIDNEY DISEASE

See full prescribing information for complete boxed warning.

- Patients with advanced chronic kidney disease are at greater risk of severe hypocalcemia following denosumab products administration. Severe hypocalcemia resulting in hospitalization, life-threatening events and fatal cases have been reported. (5.1)
- The presence of chronic kidney disease-mineral bone disorder (CKD-MBD) markedly increases the risk of hypocalcemia. (5.1)
- Prior to initiating Boncresa in patients with advanced chronic kidney disease, evaluate for the presence of CKD-MBD. Treatment with Boncresa in these patients should be supervised by a healthcare provider with expertise in the diagnosis and management of CKD-MBD. (2.2), (5.1)

1 INDICATIONS AND USAGE

Boncresa is a RANK ligand (RANKL) inhibitor indicated for treatment:

- of postmenopausal women with osteoporosis at high risk for fracture (1.1)
- to increase bone mass in men with osteoporosis at high risk for fracture (1.2)
- of glucocorticoid-induced osteoporosis in men and women at high risk for fracture (1.3)
- to increase bone mass in men at high risk for fracture receiving androgen deprivation therapy for nonmetastatic prostate cancer (1.4)
- to increase bone mass in women at high risk for fracture receiving adjuvant aromatase inhibitor therapy for breast cancer (1.5)

2 DOSAGE AND ADMINISTRATION

- Pregnancy must be ruled out prior to administration of Boncresa. (2.1)
- Before initiating Boncresa in patients with advanced chronic kidney disease, including dialysis patients, evaluate for the presence of chronic kidney disease mineral and bone disorder with intact parathyroid hormone, serum calcium, 25(OH) vitamin D, and 1,25(OH)2 vitamin D. (2.2, 5.1, 8.6)
- Boncresa should be administered by a healthcare provider. (2.3)
- Administer 60 mg every 6 months as a subcutaneous injection in the upper arm, upper thigh, or abdomen. (2.3)
- Instruct patients to take calcium 1000 mg daily and at least 400 IU vitamin D daily. (2.3)

3 DOSAGE FORMS AND STRENGTHS

- Injection: 60 mg/mL solution in a single-dose prefilled syringe (3)

4 CONTRAINDICATIONS

- Hypocalcemia (4, 5.1)
- Pregnancy (4, 8.1)
- Known hypersensitivity to denosumab products (4, 5.3)

5 WARNINGS AND PRECAUTIONS

- Same Active Ingredient: Patients receiving Boncresa should not receive other denosumab products concomitantly. (5.2)
- Hypersensitivity including anaphylactic reactions may occur. Discontinue permanently if a clinically significant reaction occurs. (5.3)
- Hypocalcemia: Pre-existing hypocalcemia must be corrected before initiating Boncresa. May worsen, especially in patients with renal impairment. Adequately supplement all patients with calcium and vitamin D. Concomitant use of calcimimetic drugs may also worsen hypocalcemia risk. Evaluate for presence of chronic kidney disease mineral-bone disorder. Monitor serum calcium. (5.1)
- Osteonecrosis of the jaw: Has been reported with denosumab products. Monitor for symptoms. (5.4)
- Atypical femoral fractures: Have been reported. Evaluate patients with thigh or groin pain to rule out a femoral fracture. (5.5)
- Multiple vertebral fractures have been reported following Boncresa discontinuation. Patients should be transitioned to another antiresorptive agent if Boncresa is discontinued. (5.6)
- Serious infections including skin infections: May occur, including those leading to hospitalization. Advise patients to seek prompt medical attention if they develop signs or symptoms of infection, including cellulitis. (5.7)
- Dermatologic reactions: Dermatitis, rashes, and eczema have been reported. Consider discontinuing Boncresa if severe symptoms develop. (5.8)
- Severe bone, joint, muscle pain may occur. Discontinue use if severe symptoms develop. (5.9)
- Suppression of bone turnover: Significant suppression has been demonstrated. Monitor for consequences of bone over-suppression. (5.10)

6 ADVERSE REACTIONS

- Postmenopausal osteoporosis: Most common adverse reactions (> 5% and more common than placebo) were: back pain, pain in extremity, hypercholesterolemia, musculoskeletal pain, and cystitis. Pancreatitis has been reported in clinical trials. (6.1)
- Male osteoporosis: Most common adverse reactions (> 5% and more common than placebo) were: back pain, arthralgia, and nasopharyngitis. (6.1)
- Glucocorticoid-induced osteoporosis: Most common adverse reactions (> 3% and more common than active-control group) were: back pain, hypertension, bronchitis, and headache. (6.1)
- Bone loss due to hormone ablation for cancer: Most common adverse reactions (≥ 10% and more common than placebo) were: arthralgia and back pain. Pain in extremity and musculoskeletal pain have also been reported in clinical trials. (6.1)

To report SUSPECTED ADVERSE REACTIONS, contact Amneal Pharmaceuticals LLC at 1-877-835-5472 or FDA at 1-800-FDA-1088 or www.fda.gov/medwatch.

8 USE IN SPECIFIC POPULATIONS

- Pregnant women and females of reproductive potential: Denosumab products may cause fetal harm when administered to pregnant women. Advise females of reproductive potential to use effective contraception during therapy, and for at least 5 months after the last dose of Boncresa. (8.1, 8.3)
- Pediatric patients: Boncresa is not approved for use in pediatric patients. (8.4)
- Renal impairment: No dose adjustment is necessary in patients with renal impairment. Patients with advanced chronic kidney disease (eGFR <30 mL/min/1.73 m^2), including dialysis-dependent patients, are at greater risk of severe hypocalcemia. The presence of underlying chronic kidney disease-mineral bone disorder markedly increases the risk of hypocalcemia. (5.1, 8.6)

*Biosimilar means that the biological product is approved based on data demonstrating that it is highly similar to an FDA-approved biological product, known as a reference product, and that there are no clinically meaningful differences between the biosimilar product and the reference product. Biosimilarity of BONCRESA has been demonstrated for the condition(s) of use (e.g., indication(s), dosing regimen(s), strength(s), dosage form(s), and route(s) of administration described in its Full Prescribing Information.

FULL PRESCRIBING INFORMATION

WARNING: SEVERE HYPOCALCEMIA IN PATIENTS WITH ADVANCED KIDNEY DISEASE

- Patients with advanced chronic kidney disease (eGFR <30 mL/min/1.73 m^2), including dialysis-dependent patients, are at greater risk of severe hypocalcemia following denosumab products administration. Severe hypocalcemia resulting in hospitalization, life-threatening events and fatal cases have been reported [see Warnings and Precautions (5.1)].
- The presence of chronic kidney disease-mineral bone disorder (CKD-MBD) markedly increases the risk of hypocalcemia in these patients [see Warnings and Precautions (5.1)].
- Prior to initiating Boncresa in patients with advanced chronic kidney disease, evaluate for the presence of CKD-MBD. Treatment with Boncresa in these patients should be supervised by a healthcare provider with expertise in the diagnosis and management of CKD-MBD [see Dosage and Administration (2.2) and Warnings and Precautions (5.1)].

1 INDICATIONS AND USAGE

1.1 Treatment of Postmenopausal Women with Osteoporosis at High Risk for Fracture

Boncresa is indicated for the treatment of postmenopausal women with osteoporosis at high risk for fracture, defined as a history of osteoporotic fracture, or multiple risk factors for fracture; or patients who have failed or are intolerant to other available osteoporosis therapy. In postmenopausal women with osteoporosis, denosumab reduces the incidence of vertebral, nonvertebral, and hip fractures [see Clinical Studies (14.1)].

1.2 Treatment to Increase Bone Mass in Men with Osteoporosis

Boncresa is indicated for treatment to increase bone mass in men with osteoporosis at high risk for fracture, defined as a history of osteoporotic fracture, or multiple risk factors for fracture; or patients who have failed or are intolerant to other available osteoporosis therapy [see Clinical Studies (14.2)].

1.3 Treatment of Glucocorticoid-Induced Osteoporosis

Boncresa is indicated for the treatment of glucocorticoid-induced osteoporosis in men and women at high risk of fracture who are either initiating or continuing systemic glucocorticoids in a daily dosage equivalent to 7.5 mg or greater of prednisone and expected to remain on glucocorticoids for at least 6 months. High risk of fracture is defined as a history of osteoporotic fracture, multiple risk factors for fracture, or patients who have failed or are intolerant to other available osteoporosis therapy [see Clinical Studies (14.3)].

1.4 Treatment of Bone Loss in Men Receiving Androgen Deprivation Therapy for Prostate Cancer

Boncresa is indicated as a treatment to increase bone mass in men at high risk for fracture receiving androgen deprivation therapy (ADT) for nonmetastatic prostate cancer. In these patients denosumab also reduced the incidence of vertebral fractures [see Clinical Studies (14.4)].

1.5 Treatment of Bone Loss in Women Receiving Adjuvant Aromatase Inhibitor Therapy for Breast Cancer

Boncresa is indicated as a treatment to increase bone mass in women at high risk for fracture receiving adjuvant aromatase inhibitor therapy for breast cancer [see Clinical Studies (14.5)].

2 DOSAGE AND ADMINISTRATION

2.1 Pregnancy Testing Prior to Initiation of Boncresa

Pregnancy must be ruled out prior to administration of Boncresa. Perform pregnancy testing in all females of reproductive potential prior to administration of Boncresa. Based on findings in animals, denosumab products can cause fetal harm when administered to pregnant women [see Use in Specific Populations (8.1, 8.3)].

2.2 Laboratory Testing in Patients with Advanced Chronic Kidney Disease Prior to Initiation of Boncresa

In patients with advanced chronic kidney disease [i.e., estimated glomerular filtration rate (eGFR) <30 mL/min/1.73 m^2], including dialysis-dependent patients, evaluate for the presence of chronic kidney disease mineral and bone disorder (CKD-MBD) with intact parathyroid hormone (iPTH), serum calcium, 25(OH) vitamin D, and 1,25 (OH)2 vitamin D prior to decisions regarding Boncresa treatment. Consider also assessing bone turnover status (serum markers of bone turnover or bone biopsy) to evaluate the underlying bone disease that may be present [see Warnings and Precautions (5.1)].

2.3 Recommended Dosage

Boncresa should be administered by a healthcare provider.

The recommended dose of Boncresa is 60 mg administered as a single subcutaneous injection once every 6 months. Administer Boncresa via subcutaneous injection in the upper arm, the upper thigh, or the abdomen. All patients should receive calcium 1000 mg daily and at least 400 IU vitamin D daily [see Warnings and Precautions (5.1)].

If a dose of Boncresa is missed, administer the injection as soon as the patient is available. Thereafter, schedule injections every 6 months from the date of the last injection.

2.4 Preparation and Administration

Parenteral drug products should be inspected visually for particulate matter and discoloration prior to administration whenever solution and container permit. Boncresais a clear, colorless to pale yellow solution. Do not use if the solution is discolored or cloudy or if the solution contains visible particles or foreign particulate matter.

Prior to administration, Boncresamay be removed from the refrigerator and brought to room temperature up to 25°C (77°F) by standing in the original container. This generally takes 15 to 30 minutes. Do not warm Boncresain any other way [see How Supplied/Storage and Handling (16)].

Instructions for Administration of Boncresa Prefilled Syringe with Needle Safety Guard

IMPORTANT: In order to minimize accidental needlesticks, the Boncresasingle-dose prefilled syringe has a transparent safety guard, which is automatically activated after the injection.

DO NOT attempt to activate the transparent safety guard before injection.

Step 1: Remove Gray Needle Cap

Step 2: Administer Subcutaneous Injection

Choose an injection site. The recommended injection sites for Boncresa include: the upper arm OR the upper thigh OR the abdomen.

Insert needle and inject all the liquid subcutaneously into pinched skin. Do not administer into muscle or blood vessels.

Slowly push the plunger all the way down until all the liquid is injected and the transparent safety guard is automatically activated.

Step 3: Release Plunger and Remove the Syringe From Skin

Release your thumb upwards from the plunger. This will allow the needle to move automatically up into the transparent safety guard. Then lift the syringe from the skin.

Immediately dispose of the syringe and gray needle cap in the nearest sharps container. Do not put the needle cap back on the used syringe.

3 DOSAGE FORMS AND STRENGTHS

- Injection: 60 mg/mL clear, colorless to pale yellow solution in a single-dose prefilled syringe.

4 CONTRAINDICATIONS

Boncresa is contraindicated in:

- Patients with hypocalcemia: Pre-existing hypocalcemia must be corrected prior to initiating therapy with Boncresa [see Warnings and Precautions (5.1)].
- Pregnant women: Denosumab products may cause fetal harm when administered to a pregnant woman. In women of reproductive potential, pregnancy testing should be performed prior to initiating treatment with Boncresa [see Use in Specific Populations (8.1)].
- Patients with hypersensitivity to denosumab products: Boncresa is contraindicated in patients with a history of systemic hypersensitivity to any component of the product. Reactions have included anaphylaxis, facial swelling, and urticaria [see Warnings and Precautions (5.3) andAdverse Reactions (6.2)].

5 WARNINGS AND PRECAUTIONS

5.1 Severe Hypocalcemia and Mineral Metabolism Changes

Denosumab products can cause severe hypocalcemia and fatal cases have been reported. Pre-existing hypocalcemia must be corrected prior to initiating therapy with Boncresa. Adequately supplement all patients with calcium and vitamin D [see Dosage and Administration (2.1), Contraindications (4), andAdverse Reactions (6.1)].

In patients without advanced chronic kidney disease who are predisposed to hypocalcemia and disturbances of mineral metabolism (e.g., history of hypoparathyroidism, thyroid surgery, parathyroid surgery, malabsorption syndromes, excision of small intestine, treatment with other calcium-lowering drugs), assess serum calcium and mineral levels (phosphorus and magnesium) 10 to14 days after Boncresa injection. In some postmarketing cases, hypocalcemia persisted for weeks or months and required frequent monitoring and intravenous and/or oral calcium replacement, with or without vitamin D.

Patients with Advanced Chronic Kidney Disease

Patients with advanced chronic kidney disease [i.e., eGFR <30 mL/min/1.73 m^2] including dialysis-dependent patients are at greater risk for severe hypocalcemia following denosumab products administration. Severe hypocalcemia resulting in hospitalization, life-threatening events and fatal cases have been reported. The presence of underlying chronic kidney disease-mineral bone disorder (CKD-MBD, renal osteodystrophy) markedly increases the risk of hypocalcemia. Concomitant use of calcimimetic drugs may also worsen hypocalcemia risk.

To minimize the risk of hypocalcemia in patients with advanced chronic kidney disease, evaluate for the presence of chronic kidney disease mineral and bone disorder with intact parathyroid hormone (iPTH), serum calcium, 25(OH) vitamin D, and 1,25(OH)2 vitamin D prior to decisions regarding Boncresa treatment. Consider also assessing bone turnover status (serum markers of bone turnover or bone biopsy) to evaluate the underlying bone disease that may be present. Monitor serum calcium weekly for the first month after Boncresa administration and monthly thereafter. Instruct all patients with advanced chronic kidney disease, including those who are dialysis-dependent, about the symptoms of hypocalcemia and the importance of maintaining serum calcium levels with adequate calcium and activated vitamin D supplementation. Treatment with Boncresa in these patients should be supervised by a healthcare provider who is experienced in diagnosis and management of CKD-MBD.

5.2 Drug Products with Same Active Ingredient

Patients receiving Boncresa should not receive other denosumab products concomitantly.

5.3 Hypersensitivity

Clinically significant hypersensitivity including anaphylaxis has been reported with denosumab products. Symptoms have included hypotension, dyspnea, throat tightness, facial and upper airway edema, pruritus, and urticaria. If an anaphylactic or other clinically significant allergic reaction occurs, initiate appropriate therapy and discontinue further use of Boncresa [see Contraindications (4) and Adverse Reactions (6.2)].

5.4 Osteonecrosis of the Jaw

Osteonecrosis of the jaw (ONJ), which can occur spontaneously, is generally associated with tooth extraction and/or local infection with delayed healing. ONJ has been reported in patients receiving denosumab products [see Adverse Reactions (6.1)]. A routine oral exam should be performed by the prescriber prior to initiation of Boncresa treatment. A dental examination with appropriate preventive dentistry is recommended prior to treatment with Boncresa in patients with risk factors for ONJ such as invasive dental procedures (e.g., tooth extraction, dental implants, oral surgery), diagnosis of cancer, concomitant therapies (e.g., chemotherapy, corticosteroids, angiogenesis inhibitors), poor oral hygiene, and comorbid disorders (e.g., periodontal and/or other pre-existing dental disease, anemia, coagulopathy, infection, ill-fitting dentures). Good oral hygiene practices should be maintained during treatment with Boncresa. Concomitant administration of drugs associated with ONJ may increase the risk of developing ONJ. The risk of ONJ may increase with duration of exposure to denosumab products.

For patients requiring invasive dental procedures, clinical judgment of the treating physician and/or oral surgeon should guide the management plan of each patient based on individual benefit-risk assessment.

Patients who are suspected of having or who develop ONJ while on Boncresa should receive care by a dentist or an oral surgeon. In these patients, extensive dental surgery to treat ONJ may exacerbate the condition. Discontinuation of Boncresa therapy should be considered based on individual benefit-risk assessment.

5.5 Atypical Subtrochanteric and Diaphyseal Femoral Fractures

Atypical low energy or low trauma fractures of the shaft have been reported in patients receiving denosumab products [see Adverse Reactions (6.1)]. These fractures can occur anywhere in the femoral shaft from just below the lesser trochanter to above the supracondylar flare and are transverse or short oblique in orientation without evidence of comminution. Causality has not been established as these fractures also occur in osteoporotic patients who have not been treated with antiresorptive agents.

Atypical femoral fractures most commonly occur with minimal or no trauma to the affected area. They may be bilateral, and many patients report prodromal pain in the affected area, usually presenting as dull, aching thigh pain, weeks to months before a complete fracture occurs. A number of reports note that patients were also receiving treatment with glucocorticoids (e.g., prednisone) at the time of fracture.

During Boncresa treatment, patients should be advised to report new or unusual thigh, hip, or groin pain. Any patient who presents with thigh or groin pain should be suspected of having an atypical fracture and should be evaluated to rule out an incomplete femur fracture. Patients presenting with an atypical femur fracture should also be assessed for symptoms and signs of fracture in the contralateral limb. Interruption of Boncresa therapy should be considered, pending a benefit-risk assessment, on an individual basis.

5.6 Multiple Vertebral Fractures (MVF) Following Treatment Discontinuation

Following discontinuation of denosumab treatment, fracture risk increases, including the risk of multiple vertebral fractures. Treatment with denosumab results in significant suppression of bone turnover and cessation of denosumab treatment results in increased bone turnover above pretreatment values 9 months after the last dose of denosumab. Bone turnover then returns to pretreatment values 24 months after the last dose of denosumab. In addition, bone mineral density (BMD) returns to pretreatment values within 18 months after the last injection [see Clinical Pharmacology (12.2) and Clinical Studies (14.1)].

New vertebral fractures occurred as early as 7 months (on average 19 months) after the last dose of denosumab. Prior vertebral fracture was a predictor of multiple vertebral fractures after denosumab discontinuation. Evaluate an individual’s benefit-risk before initiating treatment with Boncresa.

If Boncresa treatment is discontinued, patients should be transitioned to an alternative antiresorptive therapy [see Adverse Reactions (6.1)].

5.7 Serious Infections

In a clinical trial of over 7800 women with postmenopausal osteoporosis, serious infections leading to hospitalization were reported more frequently in the denosumab group than in the placebo group [see Adverse Reactions (6.1)]. Serious skin infections, as well as infections of the abdomen, urinary tract, and ear, were more frequent in patients treated with denosumab. Endocarditis was also reported more frequently in denosumab-treated patients. The incidence of opportunistic infections was similar between placebo and denosumab groups, and the overall incidence of infections was similar between the treatment groups. Advise patients to seek prompt medical attention if they develop signs or symptoms of severe infection, including cellulitis.

Patients on concomitant immunosuppressant agents or with impaired immune systems may be at increased risk for serious infections. Consider the benefit-risk profile in such patients before treating with Boncresa. In patients who develop serious infections while on Boncresa, prescribers should assess the need for continued Boncresa therapy.

5.8 Dermatologic Adverse Reactions

In a large clinical trial of over 7800 women with postmenopausal osteoporosis, epidermal and dermal adverse events such as dermatitis, eczema, and rashes occurred at a significantly higher rate in the denosumab group compared to the placebo group. Most of these events were not specific to the injection site [see Adverse Reactions (6.1)]. Consider discontinuing Boncresa if severe symptoms develop.

5.9 Musculoskeletal Pain

In postmarketing experience, severe and occasionally incapacitating bone, joint, and/or muscle pain has been reported in patients taking denosumab products [see Adverse Reactions (6.2)]. The time to onset of symptoms varied from one day to several months after starting denosumab products. Consider discontinuing use if severe symptoms develop [see Patient Counseling Information (17)].

5.10 Suppression of Bone Turnover

In clinical trials in women with postmenopausal osteoporosis, treatment with denosumab resulted in significant suppression of bone remodeling as evidenced by markers of bone turnover and bone histomorphometry [see Clinical Pharmacology (12.2) and Clinical Studies (14.1)]. The significance of these findings and the effect of long-term treatment with denosumab products are unknown. The long-term consequences of the degree of suppression of bone remodeling observed with denosumab may contribute to adverse outcomes such as osteonecrosis of the jaw, atypical fractures, and delayed fracture healing. Monitor patients for these consequences.

5.11 Hypercalcemia in Pediatric Patients with Osteogenesis Imperfecta

Boncresa is not approved for use in pediatric patients. Hypercalcemia has been reported in pediatric patients with osteogenesis imperfecta treated with denosumab products. Some cases required hospitalization [see Use in Specific Populations (8.4)].

6 ADVERSE REACTIONS

The following serious adverse reactions are discussed below and also elsewhere in the labeling:

- Severe Hypocalcemia and Mineral Metabolism Changes [see Warnings and Precautions (5.1)]
- Hypersensitivity [see Warnings and Precautions (5.3)]
- Osteonecrosis of the Jaw [see Warnings and Precautions (5.4)]
- Atypical Subtrochanteric and Diaphyseal Femoral Fractures [see Warnings and Precautions (5.5)]
- Multiple Vertebral Fractures (MVF) Following Treatment Discontinuation [see Warnings and Precautions (5.6)]
- Serious Infections [see Warnings and Precautions (5.7)]
- Dermatologic Adverse Reactions [see Warnings and Precautions (5.8)]

The most common adverse reactions reported with denosumab products in patients with postmenopausal osteoporosis are back pain, pain in extremity, musculoskeletal pain, hypercholesterolemia, and cystitis.

The most common adverse reactions reported with denosumab products in men with osteoporosis are back pain, arthralgia, and nasopharyngitis.

The most common adverse reactions reported with denosumab products in patients with glucocorticoid-induced osteoporosis are back pain, hypertension, bronchitis, and headache.

The most common (per patient incidence ≥ 10%) adverse reactions reported with denosumab products in patients with bone loss receiving androgen deprivation therapy for prostate cancer or adjuvant aromatase inhibitor therapy for breast cancer are arthralgia and back pain. Pain in extremity and musculoskeletal pain have also been reported in clinical trials.

The most common adverse reactions leading to discontinuation of denosumab products in patients with postmenopausal osteoporosis are back pain and constipation.

6.1 Clinical Trials Experience

Because clinical studies are conducted under widely varying conditions, adverse reaction rates observed in the clinical studies of a drug cannot be directly compared to rates in the clinical studies of another drug and may not reflect the rates observed in clinical practice.

Treatment of Postmenopausal Women with Osteoporosis

The safety of denosumab in the treatment of postmenopausal osteoporosis was assessed in a 3-year, randomized, double-blind, placebo-controlled, multinational study of 7808 postmenopausal women aged 60 to 91 years. A total of 3876 women were exposed to placebo and 3886 women were exposed to denosumab administered subcutaneously once every 6 months as a single 60 mg dose. All women were instructed to take at least 1000 mg of calcium and 400 IU of vitamin D supplementation per day.

The incidence of all-cause mortality was 2.3% (n = 90) in the placebo group and 1.8% (n = 70) in the denosumab group. The incidence of nonfatal serious adverse events was 24.2% in the placebo group and 25.0% in the denosumab group. The percentage of patients who withdrew from the study due to adverse events was 2.1% and 2.4% for the placebo and denosumab groups, respectively. The most common adverse reactions reported with denosumab in patients with postmenopausal osteoporosis are back pain, pain in extremity, musculoskeletal pain, hypercholesterolemia, and cystitis.

Adverse reactions reported in ≥ 2% of postmenopausal women with osteoporosis and more frequently in the denosumab-treated women than in the placebo-treated women are shown in the table below.

Table 1. Adverse Reactions Occurring in ≥ 2% of Patients with Osteoporosis and More Frequently than in Placebo-treated Patients

Preferred Term | Denosumab (N = 3886); n (%) | Placebo; (N = 3876); n (%)
Back pain | 1347 (34.7) | 1340 (34.6)
Pain in extremity | 453 (11.7) | 430 (11.1)
Musculoskeletal pain | 297 (7.6) | 291 (7.5)
Hypercholesterolemia | 280 (7.2) | 236 (6.1)
Cystitis | 228 (5.9) | 225 (5.8)
Vertigo | 195 (5.0) | 187 (4.8)
Upper respiratory tract infection | 190 (4.9) | 167 (4.3)
Edema peripheral | 189 (4.9) | 155 (4.0)
Sciatica | 178 (4.6) | 149 (3.8)
Bone pain | 142 (3.7) | 117 (3.0)
Abdominal pain upper | 129 (3.3) | 111 (2.9)
Anemia | 129 (3.3) | 107 (2.8)
Insomnia | 126 (3.2) | 122 (3.1)
Myalgia | 114 (2.9) | 94 (2.4)
Angina pectoris | 101 (2.6) | 87 (2.2)
Rash | 96 (2.5) | 79 (2.0)
Pharyngitis | 91 (2.3) | 78 (2.0)
Asthenia | 90 (2.3) | 73 (1.9)
Pruritus | 87 (2.2) | 82 (2.1)
Flatulence | 84 (2.2) | 53 (1.4)
Spinal osteoarthritis | 82 (2.1) | 64 (1.7)
Gastroesophageal reflux disease | 80 (2.1) | 66 (1.7)
Herpes zoster | 79 (2.0) | 72 (1.9)

Hypocalcemia

Decreases in serum calcium levels to less than 8.5 mg/dL at any visit were reported in 0.4% women in the placebo group and 1.7% women in the denosumab group. The nadir in serum calcium level occurred at approximately day 10 after denosumab dosing in subjects with normal renal function.

In clinical studies, subjects with impaired renal function were more likely to have greater reductions in serum calcium levels compared to subjects with normal renal function. In a study of 55 subjects with varying degrees of renal function, serum calcium levels < 7.5 mg/dL or symptomatic hypocalcemia were observed in 5 subjects. These included no subjects in the normal renal function group, 10% of subjects in the creatinine clearance 50 to 80 mL/min group, 29% of subjects in the creatinine clearance < 30 mL/min group, and 29% of subjects in the hemodialysis group. These subjects did not receive calcium and vitamin D supplementation. In a study of 4550 postmenopausal women with osteoporosis, the mean change from baseline in serum calcium level 10 days after denosumab dosing was -5.5% in subjects with creatinine clearance < 30 mL/min vs. -3.1% in subjects with creatinine clearance ≥ 30 mL/min.

Serious Infections

Receptor activator of nuclear factor kappa-B ligand (RANKL) is expressed on activated T and B lymphocytes and in lymph nodes. Therefore, a RANKL inhibitor such as denosumab products may increase the risk of infection.

In the clinical study of 7808 postmenopausal women with osteoporosis, the incidence of infections resulting in death was 0.2% in both placebo and denosumab treatment groups. However, the incidence of nonfatal serious infections was 3.3% in the placebo and 4.0% in the denosumab groups. Hospitalizations due to serious infections in the abdomen (0.7% placebo vs. 0.9% denosumab), urinary tract (0.5% placebo vs. 0.7% denosumab), and ear (0.0% placebo vs. 0.1% denosumab) were reported. Endocarditis was reported in no placebo patients and 3 patients receiving denosumab.

Skin infections, including erysipelas and cellulitis, leading to hospitalization were reported more frequently in patients treated with denosumab (< 0.1% placebo vs. 0.4% denosumab).

The incidence of opportunistic infections was similar to that reported with placebo.

Dermatologic Adverse Reactions

A significantly higher number of patients treated with denosumab developed epidermal and dermal adverse events (such as dermatitis, eczema, and rashes), with these events reported in 8.2% of the placebo and 10.8% of the denosumab groups (p < 0.0001). Most of these events were not specific to the injection site [see Warnings and Precautions (5.8)].

Osteonecrosis of the Jaw

ONJ has been reported in the osteoporosis clinical trial program in patients treated with denosumab [see Warnings and Precautions (5.4)].

Atypical Subtrochanteric and Diaphyseal Femoral Fractures

In the osteoporosis clinical trial program, atypical femoral fractures were reported in patients treated with denosumab. The duration of denosumab exposure to time of atypical femoral fracture diagnosis was as early as 2&frac12; years [see Warnings and Precautions (5.5)].

Multiple Vertebral Fractures (MVF) Following Treatment Discontinuation

In the osteoporosis clinical trial program, multiple vertebral fractures were reported in patients after discontinuation of denosumab. In the phase 3 trial in women with postmenopausal osteoporosis, 6% of women who discontinued denosumab and remained in the study developed new vertebral fractures, and 3% of women who discontinued denosumab and remained in the study developed multiple new vertebral fractures. The mean time to onset of multiple vertebral fractures was 17 months (range: 7 to 43 months) after the last injection of denosumab. Prior vertebral fracture was a predictor of multiple vertebral fractures after discontinuation [see Warnings and Precautions (5.6)].

Pancreatitis

Pancreatitis was reported in 4 patients (0.1%) in the placebo and 8 patients (0.2%) in the denosumab groups. Of these reports, 1 patient in the placebo group and all 8 patients in the denosumab group had serious events, including one death in the denosumab group. Several patients had a prior history of pancreatitis. The time from product administration to event occurrence was variable.

New Malignancies

The overall incidence of new malignancies was 4.3% in the placebo and 4.8% in the denosumab groups. New malignancies related to the breast (0.7% placebo vs. 0.9% denosumab), reproductive system (0.2% placebo vs. 0.5% denosumab), and gastrointestinal system (0.6% placebo vs. 0.9% denosumab) were reported. A causal relationship to drug exposure has not been established.

Treatment to Increase Bone Mass in Men with Osteoporosis

The safety of denosumab in the treatment of men with osteoporosis was assessed in a 1-year randomized, double-blind, placebo-controlled study. A total of 120 men were exposed to placebo and 120 men were exposed to denosumab administered subcutaneously once every 6 months as a single 60 mg dose. All men were instructed to take at least 1000 mg of calcium and 800 IU of vitamin D supplementation per day.

The incidence of all-cause mortality was 0.8% (n = 1) in the placebo group and 0.8% (n = 1) in the denosumab group. The incidence of nonfatal serious adverse events was 7.5% in the placebo group and 8.3% in the denosumab group. The percentage of patients who withdrew from the study due to adverse events was 0% and 2.5% for the placebo and denosumab groups, respectively.

Adverse reactions reported in ≥ 5% of men with osteoporosis and more frequently with denosumab than in the placebo-treated patients were: back pain (6.7% placebo vs. 8.3% denosumab), arthralgia (5.8% placebo vs. 6.7% denosumab), and nasopharyngitis (5.8% placebo vs. 6.7% denosumab).

Serious Infections

Serious infection was reported in 1 patient (0.8%) in the placebo group and no patients in the denosumab group.

Dermatologic Adverse Reactions

Epidermal and dermal adverse events (such as dermatitis, eczema, and rashes) were reported in 4 patients (3.3%) in the placebo group and 5 patients (4.2%) in the denosumab group.

Osteonecrosis of the Jaw

No cases of ONJ were reported.

Pancreatitis

Pancreatitis was reported in 1 patient (0.8%) in the placebo group and 1 patient (0.8%) in the denosumab group.

New Malignancies

New malignancies were reported in no patients in the placebo group and 4 (3.3%) patients (3 prostate cancers, 1 basal cell carcinoma) in the denosumab group.

Treatment of Glucocorticoid-Induced Osteoporosis

The safety of denosumab in the treatment of glucocorticoid-induced osteoporosis was assessed in the 1-year, primary analysis of a 2-year randomized, multicenter, double-blind, parallel-group, active-controlled study of 795 patients (30% men and 70% women) aged 20 to 94 (mean age of 63 years) treated with greater than or equal to 7.5 mg/day oral prednisone (or equivalent). A total of 384 patients were exposed to 5 mg oral daily bisphosphonate (active-control) and 394 patients were exposed to denosumab administered once every 6 months as a 60 mg subcutaneous dose. All patients were instructed to take at least 1000 mg of calcium and 800 IU of vitamin D supplementation per day.

The incidence of all-cause mortality was 0.5% (n = 2) in the active-control group and 1.5% (n = 6) in the denosumab group. The incidence of serious adverse events was 17% in the active-control group and 16% in the denosumab group. The percentage of patients who withdrew from the study due to adverse events was 3.6% and 3.8% for the active-control and denosumab groups, respectively.

Adverse reactions reported in ≥ 2% of patients with glucocorticoid-induced osteoporosis and more frequently with denosumab than in the active-control-treated patients are shown in the table below.

Table 2. Adverse Reactions Occurring in ≥ 2% of Patients with Glucocorticoid-induced Osteoporosis and More Frequently with Denosumab than in Active-Control-treated Patients

Preferred Term | Denosumab; (N = 394); n (%) | Oral Daily Bisphosphonate; (Active-Control); (N = 384); n (%)
Back pain | 18 (4.6) | 17 (4.4)
Hypertension | 15 (3.8) | 13 (3.4)
Bronchitis | 15 (3.8) | 11 (2.9)
Headache | 14 (3.6) | 7 (1.8)
Dyspepsia | 12 (3.0) | 10 (2.6)
Urinary tract infection | 12 (3.0) | 8 (2.1)
Abdominal pain upper | 12 (3.0) | 7 (1.8)
Upper respiratory tract infection | 11 (2.8) | 10 (2.6)
Constipation | 11 (2.8) | 6 (1.6)
Vomiting | 10 (2.5) | 6 (1.6)
Dizziness | 9 (2.3) | 8 (2.1)
Fall | 8 (2.0) | 7 (1.8)
Polymyalgia rheumatica* | 8 (2.0) | 1 (0.3)

*Events of worsening of underlying polymyalgia rheumatica.

Osteonecrosis of the Jaw

No cases of ONJ were reported.

Atypical Subtrochanteric and Diaphyseal Femoral Fractures

Atypical femoral fractures were reported in 1 patient treated with denosumab. The duration of denosumab exposure to time of atypical femoral fracture diagnosis was at 8.0 months [see Warnings and Precautions (5.5)].

Serious Infections

Serious infection was reported in 15 patients (3.9%) in the active-control group and 17 patients (4.3%) in the denosumab group.

Dermatologic Adverse Reactions

Epidermal and dermal adverse events (such as dermatitis, eczema, and rashes) were reported in 16 patients (4.2%) in the active-control group and 15 patients (3.8%) in the denosumab group.

Treatment of Bone Loss in Patients Receiving Androgen Deprivation Therapy for Prostate Cancer or Adjuvant Aromatase Inhibitor Therapy for Breast Cancer

The safety of denosumab in the treatment of bone loss in men with nonmetastatic prostate cancer receiving androgen deprivation therapy (ADT) was assessed in a 3-year, randomized, double-blind, placebo-controlled, multinational study of 1468 men aged 48 to 97 years. A total of 725 men were exposed to placebo and 731 men were exposed to denosumab administered once every 6 months as a single 60 mg subcutaneous dose. All men were instructed to take at least 1000 mg of calcium and 400 IU of vitamin D supplementation per day.

The incidence of serious adverse events was 30.6% in the placebo group and 34.6% in the denosumab group. The percentage of patients who withdrew from the study due to adverse events was 6.1% and 7.0% for the placebo and denosumab groups, respectively.

The safety of denosumab in the treatment of bone loss in women with nonmetastatic breast cancer receiving aromatase inhibitor (AI) therapy was assessed in a 2-year, randomized, double-blind, placebo-controlled, multinational study of 252 postmenopausal women aged 35 to 84 years. A total of 120 women were exposed to placebo and 129 women were exposed to denosumab administered once every 6 months as a single 60 mg subcutaneous dose. All women were instructed to take at least 1000 mg of calcium and 400 IU of vitamin D supplementation per day.

The incidence of serious adverse events was 9.2% in the placebo group and 14.7% in the denosumab group. The percentage of patients who withdrew from the study due to adverse events was 4.2% and 0.8% for the placebo and denosumab groups, respectively.

Adverse reactions reported in ≥ 10% of denosumab-treated patients receiving ADT for prostate cancer or adjuvant AI therapy for breast cancer, and more frequently than in the placebo-treated patients were: arthralgia (13.0% placebo vs. 14.3% denosumab) and back pain (10.5% placebo vs. 11.5% denosumab). Pain in extremity (7.7% placebo vs. 9.9% denosumab) and musculoskeletal pain (3.8% placebo vs. 6.0% denosumab) have also been reported in clinical trials. Additionally, in denosumab-treated men with nonmetastatic prostate cancer receiving ADT, a greater incidence of cataracts was observed (1.2% placebo vs. 4.7% denosumab). Hypocalcemia (serum calcium < 8.4 mg/dL) was reported only in denosumab-treated patients (2.4% vs. 0.0%) at the month 1 visit.

6.2 Postmarketing Experience

Because postmarketing reactions are reported voluntarily from a population of uncertain size, it is not always possible to reliably estimate their frequency or establish a causal relationship to drug exposure.

The following adverse reactions have been identified during post approval use of denosumab products:

- Drug-related hypersensitivity reactions: anaphylaxis, rash, urticaria, facial swelling, and erythema
- Hypocalcemia: severe symptomatic hypocalcemia resulting in hospitalization, life-threatening events, and fatal cases
- Musculoskeletal pain, including severe cases
- Parathyroid hormone (PTH): Marked elevation in serum PTH in patients with severe renal impairment (creatinine clearance < 30 mL/min) or receiving dialysis
- Multiple vertebral fractures following treatment discontinuation
- Cutaneous and mucosal lichenoid drug eruptions (e.g., lichen planus-like reactions)
- Alopecia
- Vasculitis (e.g., ANCA positive vasculitis, leukocytoclastic vasculitis)
- Drug reaction with eosinophilia and systemic symptoms (DRESS) syndrome

8 USE IN SPECIFIC POPULATIONS

8.1 Pregnancy

Risk Summary

Boncresa is contraindicated for use in pregnant women because it may cause harm to a fetus. There are insufficient data with denosumab products use in pregnant women to inform any drug-associated risks for adverse developmental outcomes. In utero denosumab exposure from cynomolgus monkeys dosed monthly with denosumab throughout pregnancy at a dose 50-fold higher than the recommended human dose based on body weight resulted in increased fetal loss, stillbirths, and postnatal mortality, and absent lymph nodes, abnormal bone growth, and decreased neonatal growth [see Data].

Data

Animal Data

The effects of denosumab on prenatal development have been studied in both cynomolgus monkeys and genetically engineered mice in which RANK ligand (RANKL) expression was turned off by gene removal (a “knockout mouse”). In cynomolgus monkeys dosed subcutaneously with denosumab throughout pregnancy starting at gestational day 20 and at a pharmacologically active dose 50-fold higher than the recommended human dose based on body weight, there was increased fetal loss during gestation, stillbirths, and postnatal mortality. Other findings in offspring included absence of axillary, inguinal, mandibular, and mesenteric lymph nodes; abnormal bone growth, reduced bone strength, reduced hematopoiesis, dental dysplasia, and tooth malalignment; and decreased neonatal growth. At birth out to 1 month of age, infants had measurable blood levels of denosumab (22% to 621% of maternal levels).

Following a recovery period from birth out to 6 months of age, the effects on bone quality and strength returned to normal; there were no adverse effects on tooth eruption, though dental dysplasia was still apparent; axillary and inguinal lymph nodes remained absent, while mandibular and mesenteric lymph nodes were present, though small; and minimal to moderate mineralization in multiple tissues was seen in one recovery animal. There was no evidence of maternal harm prior to labor; adverse maternal effects occurred infrequently during labor. Maternal mammary gland development was normal. There was no fetal NOAEL (no observable adverse effect level) established for this study because only one dose of 50 mg/kg was evaluated. Mammary gland histopathology at 6 months of age was normal in female offspring exposed to denosumab in utero; however, development and lactation have not been fully evaluated.

In RANKL knockout mice, absence of RANKL (the target of denosumab) also caused fetal lymph node agenesis and led to postnatal impairment of dentition and bone growth. Pregnant RANKL knockout mice showed altered maturation of the maternal mammary gland, leading to impaired lactation [see Use in Specific Populations (8.2) and Nonclinical Toxicology (13.2)].

The no effect dose for denosumab products-induced teratogenicity is unknown. However, a Cmax of 22.9 ng/mL was identified in cynomolgus monkeys as a level in which no biologic effects (NOEL) of denosumab were observed (no inhibition of RANKL) [see Clinical Pharmacology (12.3)].

8.2 Lactation

Risk Summary

There is no information regarding the presence of denosumab products in human milk, the effects on the breastfed infant, or the effects on milk production. Denosumab was detected in the maternal milk of cynomolgus monkeys up to 1 month after the last dose of denosumab (≤ 0.5% milk:serum ratio) and maternal mammary gland development was normal, with no impaired lactation. However, pregnant RANKL knockout mice showed altered maturation of the maternal mammary gland, leading to impaired lactation [see Use in Specific Populations (8.1) and Nonclinical Toxicology (13.2)].

8.3 Females and Males of Reproductive Potential

Based on findings in animals, denosumab products can cause fetal harm when administered to a pregnant woman [see Use in Specific Populations (8.1)].

Pregnancy Testing

Verify the pregnancy status of females of reproductive potential prior to initiating Boncresa treatment.

Contraception

Females

Advise females of reproductive potential to use effective contraception during therapy, and for at least 5 months after the last dose of Boncresa.

Males

Denosumab was present at low concentrations (approximately 2% of serum exposure) in the seminal fluid of male subjects given denosumab. Following vaginal intercourse, the maximum amount of denosumab delivered to a female partner would result in exposures approximately 11000 times lower than the prescribed 60 mg subcutaneous dose, and at least 38 times lower than the NOEL in monkeys.

Therefore, male condom use would not be necessary as it is unlikely that a female partner or fetus would be exposed to pharmacologically relevant concentrations of denosumab products via seminal fluid [see Clinical Pharmacology (12.3)].

8.4 Pediatric Use

The safety and effectiveness of Boncresa have not been established in pediatric patients

In one multicenter, open-label study with denosumab conducted in 153 pediatric patients with osteogenesis imperfecta, aged 2 to 17 years, evaluating fracture risk reduction, efficacy was not demonstrated.

Hypercalcemia has been reported in pediatric patients with osteogenesis imperfecta treated with denosumab products. Some cases required hospitalization and were complicated by acute renal injury [see Warnings and Precautions (5.11)]. Clinical studies in pediatric patients with osteogenesis imperfecta were terminated early due to the occurrence of life-threatening events and hospitalizations due to hypercalcemia.

Safety and effectiveness were not demonstrated for the treatment of glucocorticoid-induced osteoporosis in one multicenter, randomized, double-blind, placebo-controlled, parallel-group study conducted in 24 pediatric patients with glucocorticoid-induced osteoporosis, aged 5 to 17 years, evaluating change from baseline in lumbar spine BMD Z-score.

Based on results from animal studies, denosumab may negatively affect long-bone growth and dentition in pediatric patients below the age of 4 years.

Juvenile Animal Toxicity Data

Treatment with denosumab products may impair long-bone growth in children with open growth plates and may inhibit eruption of dentition. In neonatal rats, inhibition of RANKL (the target of denosumab therapy) with a construct of osteoprotegerin bound to Fc (OPG-Fc) at doses ≤ 10 mg/kg was associated with inhibition of bone growth and tooth eruption. Adolescent primates treated with denosumab at doses 10 and 50 times (10 and 50 mg/kg dose) higher than the recommended human dose of 60 mg administered every 6 months, based on body weight (mg/kg), had abnormal growth plates, considered to be consistent with the pharmacological activity of denosumab [see Nonclinical Toxicology (13.2)].

Cynomolgus monkeys exposed in utero to denosumab exhibited bone abnormalities, an absence of axillary, inguinal, mandibular, and mesenteric lymph nodes, reduced hematopoiesis, tooth malalignment, and decreased neonatal growth. Some bone abnormalities recovered once exposure was ceased following birth; however, axillary and inguinal lymph nodes remained absent 6 months post-birth [see Use in Specific Populations (8.1)].

8.5 Geriatric Use

Of the total number of patients in clinical studies of denosumab, 9943 patients (76%) were ≥ 65 years old, while 3576 (27%) were ≥ 75 years old. Of the patients in the osteoporosis study in men, 133 patients (55%) were ≥ 65 years old, while 39 patients (16%) were ≥ 75 years old. Of the patients in the glucocorticoid-induced osteoporosis study, 355 patients (47%) were ≥ 65 years old, while 132 patients (17%) were ≥ 75 years old. No overall differences in safety or efficacy were observed between these patients and younger patients, and other reported clinical experience has not identified differences in responses between the elderly and younger patients, but greater sensitivity of some older individuals cannot be ruled out.

8.6 Renal Impairment

No dose adjustment is necessary in patients with renal impairment.

Severe hypocalcemia resulting in hospitalization, life-threatening events and fatal cases have been reported postmarketing. In clinical studies, patients with advanced chronic kidney disease (i.e., eGFR < 30 mL/min/1.73 m^2), including dialysis-dependent patients, were at greater risk of developing hypocalcemia. The presence of underlying chronic kidney disease-mineral bone disorder (CKD-MBD, renal osteodystrophy) markedly increases the risk of hypocalcemia. Concomitant use of calcimimetic drugs may also worsen hypocalcemia risk. Consider the benefits and risks to the patient when administering Boncresa to patients with advanced chronic kidney disease. Monitor calcium and mineral levels (phosphorus and magnesium). Adequate intake of calcium and vitamin D is important in patients with advanced chronic kidney disease including dialysis-dependent patients [see Dosage and Administration (2.2), Warnings and Precautions (5.1), Adverse Reactions (6.1) andClinical Pharmacology (12.3)].

11 DESCRIPTION

Denosumab-mobz is a human IgG2 monoclonal antibody with affinity and specificity for human RANKL (receptor activator of nuclear factor kappa-B ligand). Denosumab-mobz has an approximate molecular weight of 147 kDa and is produced in genetically engineered mammalian (Chinese hamster ovary) cells.

Boncresa(denosumab-mobz) injection is a sterile, preservative-free, clear, colorless to pale yellow solution for subcutaneous use.

Each single-dose prefilled syringe contains 1 mL solution of 60 mg denosumab-mobz (60 mg/mL solution), glacial acetic acid (1 mg), polysorbate 20 (0.1 mg), sorbitol (46 mg), Water for Injection (USP), and sodium hydroxide to adjust the pH to 5.2.

12 CLINICAL PHARMACOLOGY

12.1 Mechanism of Action

Denosumab productsbinds to RANKL, a transmembrane or soluble protein essential for the formation, function, and survival of osteoclasts, the cells responsible for bone resorption. Denosumab productsprevent RANKL from activating its receptor, RANK, on the surface of osteoclasts and their precursors. Prevention of the RANKL/RANK interaction inhibits osteoclast formation, function, and survival, thereby decreasing bone resorption and increasing bone mass and strength in both cortical and trabecular bone.

12.2 Pharmacodynamics

In clinical studies, treatment with 60 mg of denosumab resulted in reduction in the bone resorption marker serum type 1 C-telopeptide (CTX) by approximately 85% by 3 days, with maximal reductions occurring by 1 month. CTX levels were below the limit of assay quantitation (0.049 ng/mL) in 39% to 68% of patients 1 to 3 months after dosing of denosumab. At the end of each dosing interval, CTX reductions were partially attenuated from a maximal reduction of ≥ 87% to ≥ 45% (range: 45% to 80%), as serum denosumab levels diminished, reflecting the reversibility of the effects of denosumab on bone remodeling. These effects were sustained with continued treatment. Upon reinitiation, the degree of inhibition of CTX by denosumab was similar to that observed in patients initiating denosumab treatment.

Consistent with the physiological coupling of bone formation and resorption in skeletal remodeling, subsequent reductions in bone formation markers (i.e., osteocalcin and procollagen type 1 N-terminal peptide [P1NP]) were observed starting 1 month after the first dose of denosumab. After discontinuation of denosumab therapy, markers of bone resorption increased to levels 40% to 60% above pretreatment values but returned to baseline levels within 12 months.

12.3 Pharmacokinetics

In a study conducted in healthy male and female volunteers (n = 73, age range: 18 to 64 years) following a single subcutaneously administered denosumab dose of 60 mg, the mean area-under-the-concentration-time curve up to 16 weeks (AUC0-16 weeks) of denosumab was 316 mcg⋅day/mL (standard deviation [SD] = 101 mcg⋅day/mL). The mean maximum denosumab concentration (Cmax) was 6.75 mcg/mL (SD = 1.89 mcg/mL). No accumulation or change in denosumab pharmacokinetics with time is observed with multiple dosing of 60 mg subcutaneously administered once every 6 months.

Absorption

Following subcutaneous administration, the median time to maximum denosumab concentration (Tmax) was 10 days (range: 3 to 21 days).

Distribution

The mean volume of distribution for denosumab was 5.2 L (SD = 1.7 L).

Elimination

Serum denosumab concentrations declined over a period of 4 to 5 months with a mean half-life of 25.4 days (SD = 8.5 days; n = 46).

A population pharmacokinetic analysis was performed to evaluate the effects of demographic characteristics. This analysis showed no notable differences in pharmacokinetics with age (in postmenopausal women), race, or body weight (36 to 140 kg).

Seminal Fluid Pharmacokinetic Study

Serum and seminal fluid concentrations of denosumab were measured in 12 healthy male volunteers (age range: 43 to 65 years). After a single 60 mg subcutaneous administration of denosumab, the mean (± SD) Cmax values in the serum and seminal fluid samples were 6170 (± 2070) and 100 (± 81.9) ng/mL, respectively, resulting in a maximum seminal fluid concentration of approximately 2% of serum levels. The median (range) Tmax values in the serum and seminal fluid samples were 8.0 (7.9 to 21) and 21 (8.0 to 49) days, respectively. Among the subjects, the highest denosumab concentration in seminal fluid was 301 ng/mL at 22 days post-dose. On the first day of measurement (10 days post-dose), nine of eleven subjects had quantifiable concentrations in semen. On the last day of measurement (106 days post-dose), five subjects still had quantifiable concentrations of denosumab in seminal fluid, with a mean (± SD) seminal fluid concentration of 21.1 (± 36.5) ng/mL across all subjects (n = 12).

Drug Interactions

In a study of 19 postmenopausal women with low BMD and rheumatoid arthritis treated with etanercept (50 mg subcutaneous injection once weekly), a single-dose of denosumab (60 mg subcutaneous injection) was administered 7 days after the previous dose of etanercept. No clinically significant changes in the pharmacokinetics of etanercept were observed.

Cytochrome P450 substrates

In a study of 17 postmenopausal women with osteoporosis, midazolam (2 mg oral) was administered 2 weeks after a single-dose of denosumab (60 mg subcutaneous injection), which approximates the Tmax of denosumab. Denosumab did not affect the pharmacokinetics of midazolam, which is metabolized by cytochrome P450 3A4 (CYP3A4). This indicates that denosumab products should not alter the pharmacokinetics of drugs metabolized by CYP3A4 in postmenopausal women with osteoporosis.

Specific Populations

Gender: Mean serum denosumab concentration-time profiles observed in a study conducted in healthy men ≥ 50 years were similar to those observed in a study conducted in postmenopausal women using the same dose regimen.

Age: The pharmacokinetics of denosumab were not affected by age across all populations studied whose ages ranged from 28 to 87 years.

Race: The pharmacokinetics of denosumab were not affected by race.

Renal Impairment: In a study of 55 patients with varying degrees of renal function, including patients on dialysis, the degree of renal impairment had no effect on the pharmacokinetics of denosumab; thus, dose adjustment for renal impairment is not necessary.

Hepatic Impairment: No clinical studies have been conducted to evaluate the effect of hepatic impairment on the pharmacokinetics of denosumab products.

12.6 Immunogenicity

The observed incidence of anti-drug antibodies is highly dependent on the sensitivity and specificity of the assay. Differences in assay methods preclude meaningful comparisons of the incidence of anti-drug antibodies in the studies described below with the incidence of anti-drug antibodies in other studies, including those of denosumab or of other denosumab products.

Using an electrochemiluminescent bridging immunoassay, less than 1% (55 out of 8113) of patients treated with denosumab for up to 5 years tested positive for binding antibodies (including pre-existing, transient, and developing antibodies). None of the patients tested positive for neutralizing antibodies, as was assessed using a chemiluminescent cell-based in vitro biological assay.

There was no identified clinically significant effect of anti-drug antibodies on pharmacokinetics, pharmacodynamics, safety, or effectiveness of denosumab.

13 NONCLINICAL TOXICOLOGY

13.1 Carcinogenesis and Mutagenesis and Impairment of Fertility

Carcinogenicity

The carcinogenic potential of denosumab products has not been evaluated in long-term animal studies.

Mutagenicity

The genotoxic potential of denosumab products has not been evaluated.

Impairment of Fertility

Denosumab had no effect on female fertility or male reproductive organs in monkeys at doses that were 13- to 50-fold higher than the recommended human dose of 60 mg subcutaneously administered once every 6 months, based on body weight (mg/kg).

13.2 Animal Toxicology and/or Pharmacology

Denosumab products are inhibitors of osteoclastic bone resorption via inhibition of RANKL.

In ovariectomized monkeys, once-monthly treatment with denosumab suppressed bone turnover and increased BMD and strength of cancellous and cortical bone at doses 50-fold higher than the recommended human dose of 60 mg administered once every 6 months, based on body weight (mg/kg). Bone tissue was normal with no evidence of mineralization defects, accumulation of osteoid, or woven bone.

Because the biological activity of denosumab in animals is specific to nonhuman primates, evaluation of genetically engineered (“knockout”) mice or use of other biological inhibitors of the RANK/RANKL pathway, namely OPG-Fc, provided additional information on the pharmacodynamic properties of denosumab products. RANK/RANKL knockout mice exhibited absence of lymph node formation, as well as an absence of lactation due to inhibition of mammary gland maturation (lobulo-alveolar gland development during pregnancy). Neonatal RANK/RANKL knockout mice exhibited reduced bone growth and lack of tooth eruption. A corroborative study in 2-week-old rats given the RANKL inhibitor OPG-Fc also showed reduced bone growth, altered growth plates, and impaired tooth eruption. These changes were partially reversible in this model when dosing with the RANKL inhibitors was discontinued.

14 CLINICAL STUDIES

14.1 Treatment of Postmenopausal Women with Osteoporosis

The efficacy and safety of denosumab in the treatment of postmenopausal osteoporosis was demonstrated in a 3-year, randomized, double-blind, placebo-controlled trial. Enrolled women had a baseline BMD T-score between -2.5 and -4.0 at either the lumbar spine or total hip. Women with other diseases (such as rheumatoid arthritis, osteogenesis imperfecta, and Paget’s disease) or on therapies that affect bone were excluded from this study. The 7808 enrolled women were aged 60 to 91 years with a mean age of 72 years. Overall, the mean baseline lumbar spine BMD T-score was -2.8, and 23% of women had a vertebral fracture at baseline. Women were randomized to receive subcutaneous injections of either placebo (N = 3906) or denosumab60 mg (N = 3902) once every 6 months. All women received at least 1000 mg calcium and 400 IU vitamin D supplementation daily.

The primary efficacy variable was the incidence of new morphometric (radiologically-diagnosed) vertebral fractures at 3 years. Vertebral fractures were diagnosed based on lateral spine radiographs (T4-L4) using a semiquantitative scoring method. Secondary efficacy variables included the incidence of hip fracture and nonvertebral fracture, assessed at 3 years.

Effect on Vertebral Fractures

Denosumab significantly reduced the incidence of new morphometric vertebral fractures at 1, 2, and 3 years (p < 0.0001), as shown in Table 3. The incidence of new vertebral fractures at year 3 was 7.2% in the placebo-treated women compared to 2.3% for the denosumab-treated women. The absolute risk reduction was 4.8% and relative risk reduction was 68% for new morphometric vertebral fractures at year 3.

Table 3. The Effect of Denosumab on the Incidence of New Vertebral Fractures in Postmenopausal Women

 | Proportion of Women with Fracture (%)^+ |  | Absolute Risk Reduction (%)* (95% CI) | Relative Risk Reduction (%)* (95% CI)
 | Placebo; N = 3691; (%) | Denosumab; N = 3702; (%)
0-1 Year | 2.2 | 0.9 | 1.4 (0.8, 1.9) | 61 (42, 74)
0-2 Years | 5.0 | 1.4 | 3.5 (2.7, 4.3) | 71 (61, 79)
0-3 Years | 7.2 | 2.3 | 4.8 (3.9, 5.8) | 68 (59, 74)

^+ Event rates based on crude rates in each interval.

* Absolute risk reduction and relative risk reduction based on Mantel-Haenszel method adjusting for age group variable.

Denosumab was effective in reducing the risk for new morphometric vertebral fractures regardless of age, baseline rate of bone turnover, baseline BMD, baseline history of fracture, or prior use of a drug for osteoporosis.

Effect on Hip Fractures

The incidence of hip fracture was 1.2% for placebo-treated women compared to 0.7% for denosumab-treated women at year 3. The age-adjusted absolute risk reduction of hip fractures was 0.3% with a relative risk reduction of 40% at 3 years (p = 0.04) (Figure 1).

Figure 1. Cumulative Incidence of Hip Fractures Over 3 Years

N = number of subjects randomized

Effect on Nonvertebral Fractures

Treatment with denosumab resulted in a significant reduction in the incidence of nonvertebral fractures (Table 4).

Table 4. The Effect of Denosumab on the Incidence of Nonvertebral Fractures at Year 3

 | Proportion of Women with Fracture (%)^+ |  | Absolute Risk Reduction (%) (95% CI) | Relative Risk Reduction (%) (95% CI)
 | Placebo; N = 3906; (%) | Denosumab; N = 3902; (%)
Nonvertebral fracture^1 | 8.0 | 6.5 | 1.5 (0.3, 2.7) | 20 (5, 33)*

^+ Event rates based on Kaplan-Meier estimates at 3 years. 1 Excluding those of the vertebrae (cervical, thoracic, and lumbar), skull, facial, mandible, metacarpus, and finger and toe phalanges.

* p-value = 0.01.

Effect on Bone Mineral Density (BMD)

Treatment with denosumab significantly increased BMD at all anatomic sites measured at 3 years. The treatment differences in BMD at 3 years were 8.8% at the lumbar spine, 6.4% at the total hip, and 5.2% at the femoral neck. Consistent effects on BMD were observed at the lumbar spine, regardless of baseline age, race, weight/body mass index (BMI), baseline BMD, and level of bone turnover.

After denosumab discontinuation, BMD returned to approximately baseline levels within 12 months.

Bone Histology and Histomorphometry

A total of 115 transiliac crest bone biopsy specimens were obtained from 92 postmenopausal women with osteoporosis at either month 24 and/or month 36 (53 specimens in denosumab group, 62 specimens in placebo group). Of the biopsies obtained, 115 (100%) were adequate for qualitative histology and 7 (6%) were adequate for full quantitative histomorphometry assessment.

Qualitative histology assessments showed normal architecture and quality with no evidence of mineralization defects, woven bone, or marrow fibrosis in patients treated with denosumab.

The presence of double tetracycline labeling in a biopsy specimen provides an indication of active bone remodeling, while the absence of tetracycline label suggests suppressed bone formation. In patients treated with denosumab, 35% had no tetracycline label present at the month 24 biopsy and 38% had no tetracycline label present at the month 36 biopsy, while 100% of placebo-treated patients had double label present at both time points. When compared to placebo, treatment with denosumab resulted in virtually absent activation frequency and markedly reduced bone formation rates. However, the long-term consequences of this degree of suppression of bone remodeling are unknown.

14.2 Treatment to Increase Bone Mass in Men with Osteoporosis

The efficacy and safety of denosumab in the treatment to increase bone mass in men with osteoporosis was demonstrated in a 1-year, randomized, double-blind, placebo-controlled trial. Enrolled men had a baseline BMD T-score between -2.0 and -3.5 at the lumbar spine or femoral neck. Men with a BMD T-score between -1.0 and -3.5 at the lumbar spine or femoral neck were also enrolled if there was a history of prior fragility fracture. Men with other diseases (such as rheumatoid arthritis, osteogenesis imperfecta, and Paget’s disease) or on therapies that may affect bone were excluded from this study. The 242 men enrolled in the study ranged in age from 31 to 84 years with a mean age of 65 years. Men were randomized to receive SC injections of either placebo (n = 121) or denosumab60 mg (n = 121) once every 6 months. All men received at least 1000 mg calcium and at least 800 IU vitamin D supplementation daily.

Effect on Bone Mineral Density (BMD)

The primary efficacy variable was percent change in lumbar spine BMD from baseline to 1-year. Secondary efficacy variables included percent change in total hip, and femoral neck BMD from baseline to 1-year.

Treatment with denosumab significantly increased BMD at 1-year. The treatment differences in BMD at 1-year were 4.8% (+0.9% placebo, +5.7% denosumab; (95% CI: 4.0, 5.6); p < 0.0001) at the lumbar spine, 2.0% (+0.3% placebo, +2.4% denosumab) at the total hip, and 2.2% (0.0% placebo, +2.1% denosumab) at femoral neck. Consistent effects on BMD were observed at the lumbar spine regardless of baseline age, race, BMD, testosterone concentrations, and level of bone turnover.

Bone Histology and Histomorphometry

A total of 29 transiliac crest bone biopsy specimens were obtained from men with osteoporosis at 12 months (17 specimens in denosumab group, 12 specimens in placebo group). Of the biopsies obtained, 29 (100%) were adequate for qualitative histology and, in denosumab patients, 6 (35%) were adequate for full quantitative histomorphometry assessment. Qualitative histology assessments showed normal architecture and quality with no evidence of mineralization defects, woven bone, or marrow fibrosis in patients treated with denosumab. The presence of double tetracycline labeling in a biopsy specimen provides an indication of active bone remodeling, while the absence of tetracycline label suggests suppressed bone formation. In patients treated with denosumab, 6% had no tetracycline label present at the month 12 biopsy, while 100% of placebo-treated patients had double label present. When compared to placebo, treatment with denosumab resulted in markedly reduced bone formation rates. However, the long-term consequences of this degree of suppression of bone remodeling are unknown.

14.3 Treatment of Glucocorticoid-Induced Osteoporosis

The efficacy and safety of denosumab in the treatment of patients with glucocorticoid-induced osteoporosis was assessed in the 12-month primary analysis of a 2-year, randomized, multicenter, double-blind, parallel-group, active-controlled study (NCT 01575873) of 795 patients (70% women and 30% men) aged 20 to 94 years (mean age of 63 years) treated with greater than or equal to 7.5 mg/day oral prednisone (or equivalent) for < 3 months prior to study enrollment and planning to continue treatment for a total of at least 6 months (glucocorticoid-initiating subpopulation; n = 290) or ≥ 3 months prior to study enrollment and planning to continue treatment for a total of at least 6 months (glucocorticoid-continuing subpopulation, n = 505). Enrolled patients < 50 years of age were required to have a history of osteoporotic fracture. Enrolled patients ≥ 50 years of age who were in the glucocorticoid-continuing subpopulation were required to have a baseline BMD T-score of ≤ -2.0 at the lumbar spine, total hip, or femoral neck; or a BMD T-score ≤ -1.0 at the lumbar spine, total hip, or femoral neck and a history of osteoporotic fracture.

Patients were randomized (1:1) to receive either an oral daily bisphosphonate (active-control, risedronate 5 mg once daily) (n = 397) or denosumab60 mg subcutaneously once every 6 months (n = 398) for one year. Randomization was stratified by gender within each subpopulation. Patients received at least 1000 mg calcium and 800 IU vitamin D supplementation daily.

Effect on Bone Mineral Density (BMD)

In the glucocorticoid-initiating subpopulation, denosumab significantly increased lumbar spine BMD compared to the active-control at one year (Active-control 0.8%, denosumab3.8%) with a treatment difference of 2.9% (p < 0.001). In the glucocorticoid-continuing subpopulation, denosumab significantly increased lumbar spine BMD compared to active-control at one year (Active-control 2.3%, denosumab4.4%) with a treatment difference of 2.2% (p < 0.001). Consistent effects on lumbar spine BMD were observed regardless of gender; race; geographic region; menopausal status; and baseline age, lumbar spine BMD T-score, and glucocorticoid dose within each subpopulation.

Bone Histology

Bone biopsy specimens were obtained from 17 patients (11 in the active-control treatment group and 6 in the denosumab treatment group) at Month 12. Of the biopsies obtained, 17 (100%) were adequate for qualitative histology. Qualitative assessments showed bone of normal architecture and quality without mineralization defects or bone marrow abnormality. The presence of double tetracycline labeling in a biopsy specimen provides an indication of active bone remodeling, while the absence of tetracycline label suggests suppressed bone formation. In patients treated with active-control, 100% of biopsies had tetracycline label. In patients treated with denosumab, 1 (33%) had tetracycline label and 2 (67%) had no tetracycline label present at the 12-month biopsy. Evaluation of full quantitative histomorphometry including bone remodeling rates was not possible in the glucocorticoid-induced osteoporosis population treated with denosumab. The long-term consequences of this degree of suppression of bone remodeling in glucocorticoid-treated patients is unknown.

14.4 Treatment of Bone Loss in Men with Prostate Cancer

The efficacy and safety of denosumab in the treatment of bone loss in men with nonmetastatic prostate cancer receiving androgen deprivation therapy (ADT) were demonstrated in a 3-year, randomized (1:1), double-blind, placebo-controlled, multinational study. Men less than 70 years of age had either a BMD T-score at the lumbar spine, total hip, or femoral neck between -1.0 and -4.0, or a history of an osteoporotic fracture. The mean baseline lumbar spine BMD T-score was -0.4, and 22% of men had a vertebral fracture at baseline. The 1468 men enrolled ranged in age from 48 to 97 years (median 76 years). Men were randomized to receive subcutaneous injections of either placebo (n = 734) or denosumab60 mg (n = 734) once every 6 months for a total of 6 doses. Randomization was stratified by age (< 70 years vs. ≥ 70 years) and duration of ADT at trial entry (≤ 6 months vs. > 6 months). Seventy-nine percent of patients received ADT for more than 6 months at study entry. All men received at least 1000 mg calcium and 400 IU vitamin D supplementation daily.

Effect on Bone Mineral Density (BMD)

The primary efficacy variable was percent change in lumbar spine BMD from baseline to month 24. An additional key secondary efficacy variable was the incidence of new vertebral fracture through month 36 diagnosed based on x-ray evaluation by two independent radiologists. Lumbar spine BMD was higher at 2 years in denosumab-treated patients as compared to placebo-treated patients [-1.0% placebo, +5.6% denosumab; treatment difference 6.7% (95% CI: 6.2, 7.1); p < 0.0001].

With approximately 62% of patients followed for 3 years, treatment differences in BMD at 3 years were 7.9% (-1.2% placebo, +6.8% denosumab) at the lumbar spine, 5.7% (-2.6% placebo, +3.2% denosumab) at the total hip, and 4.9% (-1.8% placebo, +3.0% denosumab) at the femoral neck. Consistent effects on BMD were observed at the lumbar spine in relevant subgroups defined by baseline age, BMD, and baseline history of vertebral fracture.

Effect on Vertebral Fractures

Denosumab significantly reduced the incidence of new vertebral fractures at 3 years (p = 0.0125), as shown in Table 5.

Table 5. The Effect of Denosumab on the Incidence of New Vertebral Fractures in Men with Nonmetastatic Prostate Cancer

Proportion of Men with Fracture; (%)^+ |  |  | Absolute Risk Reduction (%)*; (95% CI) | Relative Risk Reduction (%)*; (95% CI)
 | Placebo; N = 673; (%) | Denosumab; N = 679; (%)
0-1 Year | 1.9 | 0.3 | 1.6 (0.5, 2.8) | 85 (33, 97)
0-2 Years | 3.3 | 1.0 | 2.2 (0.7, 3.8) | 69 (27, 86)
0-3 Years | 3.9 | 1.5 | 2.4 (0.7, 4.1) | 62 (22, 81)

^+ Event rates based on crude rates in each interval.

* Absolute risk reduction and relative risk reduction based on Mantel-Haenszel method adjusting for age group and ADT duration variables.

14.5 Treatment of Bone Loss in Women with Breast Cancer

The efficacy and safety of denosumab n the treatment of bone loss in women receiving adjuvant aromatase inhibitor (AI) therapy for breast cancer was assessed in a 2-year, randomized (1:1), double-blind, placebo-controlled, multinational study. Women had baseline BMD T-scores between -1.0 to -2.5 at the lumbar spine, total hip, or femoral neck, and had not experienced fracture after age 25. The mean baseline lumbar spine BMD T-score was -1.1, and 2.0% of women had a vertebral fracture at baseline. The 252 women enrolled ranged in age from 35 to 84 years (median 59 years). Women were randomized to receive subcutaneous injections of either placebo (n = 125) or denosumab60 mg (n = 127) once every 6 months for a total of 4 doses. Randomization was stratified by duration of adjuvant AI therapy at trial entry (≤ 6 months vs. > 6 months). Sixty-two percent of patients received adjuvant AI therapy for more than 6 months at study entry. All women received at least 1000 mg calcium and 400 IU vitamin D supplementation daily.

Effect on Bone Mineral Density (BMD)

The primary efficacy variable was percent change in lumbar spine BMD from baseline to month 12. Lumbar spine BMD was higher at 12 months in denosumab-treated patients as compared to placebo-treated patients [-0.7% placebo, +4.8% denosumab; treatment difference 5.5% (95% CI: 4.8, 6.3); p < 0.0001].

With approximately 81% of patients followed for 2 years, treatment differences in BMD at 2 years were 7.6% (-1.4% placebo, +6.2% denosumab) at the lumbar spine, 4.7% (-1.0% placebo, +3.8% denosumab) at the total hip, and 3.6% (-0.8% placebo, +2.8% denosumab) at the femoral neck.

16 HOW SUPPLIED

How Supplied

Boncresa(denosumab-mobz) injection is a clear, colorless to pale yellow solution supplied in a single-dose prefilled syringe with needle safety guard. The prefilled syringe is not made with natural rubber latex.

60 mg/mL in a single-dose prefilled syringe | 1 per carton | NDC 70121-2702-1

Storage and Handling

Store Boncresa refrigerated at 2°C to 8°C (36°F to 46°F) in the original carton to protect from light. Do not freeze. Prior to administration, Boncresamay be allowed to reach room temperature up to 25°C (77°F) in the original container. Once removed from the refrigerator, Boncresa must not be exposed to temperatures above 25°C (77°F) and must be used within 14 days. Discard Boncresa if not used within the 14 days. Do not use Boncresa after the expiry date printed on the label.

Protect Boncresa from direct light and heat.

Avoid vigorous shaking of Boncresa.

17 PATIENT COUNSELING INFORMATION

Advise the patient to read the FDA-approved patient labeling (Medication Guide).

Hypocalcemia

Advise the patient to adequately supplement with calcium and vitamin D and instruct them on the importance of maintaining serum calcium levels while receiving Boncresa [see Warnings and Precautions (5.1) and Use in Specific Populations (8.6)]. Advise patients to seek prompt medical attention if they develop signs or symptoms of hypocalcemia.

Severe Hypocalcemia in Patients with Advanced Chronic Kidney Disease

Advise patients with advanced chronic kidney disease, including those who are dialysis-dependent, about the symptoms of hypocalcemia and the importance of maintaining serum calcium levels with adequate calcium and activated vitamin D supplementation. Advise these patients to have their serum calcium measured weekly for the first month after Boncresa administration and monthly thereafter. [see Dosage and Administration (2.2), Warnings and Precautions (5.1) and Use in Specific Populations (8.6)].

Drug Products with Same Active Ingredient

Advise patients that if they receive Boncresa, they should not receive other denosumab products concomitantly [see Warnings and Precautions (5.2)].

Hypersensitivity

Advise patients to seek prompt medical attention if signs or symptoms of hypersensitivity reactions occur. Advise patients who have had signs or symptoms of systemic hypersensitivity reactions that they should not receive denosumab products [see Warnings and Precautions (5.3) and Contraindications (4)].

Osteonecrosis of the Jaw

Advise patients to maintain good oral hygiene during treatment with Boncresa and to inform their dentist prior to dental procedures that they are receiving Boncresa. Patients should inform their physician or dentist

if they experience persistent pain and/or slow healing of the mouth or jaw after dental surgery [see Warnings and Precautions (5.4)].

Atypical Subtrochanteric and Diaphyseal Femoral Fractures

Advise patients to report new or unusual thigh, hip, or groin pain [see Warnings and Precautions (5.5)].

Multiple Vertebral Fractures (MVF) Following Treatment Discontinuation

Advise patients not to interrupt Boncresa therapy without talking to their physician [see Warnings and Precautions (5.6)].

Serious Infections

Advise patients to seek prompt medical attention if they develop signs or symptoms of infections,

including cellulitis [see Warnings and Precautions (5.7)].

Dermatologic Adverse Reactions

Advise patients to seek prompt medical attention if they develop signs or symptoms of dermatological

reactions (such as dermatitis, rashes, and eczema) [see Warnings and Precautions (5.8)].

Musculoskeletal Pain

Inform patients that severe bone, joint, and/or muscle pain have been reported in patients taking denosumab products.

Patients should report severe symptoms if they develop [see Warnings and Precautions (5.9)].

Pregnancy/Nursing

Counsel females of reproductive potential to use effective contraceptive measure to prevent pregnancy

during treatment and for at least 5 months after the last dose of Boncresa. Advise the patient to contact their physician immediately if pregnancy does occur during these times. Advise patients not to take Boncresa while pregnant or breastfeeding. If a patient wishes to start breastfeeding after treatment, advise her to discuss the appropriate timing with her physician [see Contraindications (4) and Use in Specific Populations (8.1)].

Schedule of Administration

Advise patients that if a dose of Boncresa is missed, the injection should be administered as soon as convenient. Thereafter, schedule injections every 6 months from the date of the last injection.

Boncresa® (denosumab)

Manufactured by:

Amneal Pharmaceuticals LLC

Piscataway, NJ 08854

Product of Spain

US License No. 2241

Medication Guide

Boncresa® (bon kree' sah)

(denosumab-mobz)

Injection, for subcutaneous use

What is the most important information I should know about Boncresa?

If you receive Boncresa, you should not receive other denosumab products at the same time.

Boncresa can cause serious side effects including:

- Increased risk of severe low calcium levels in your blood (hypocalcemia). Boncresa may lower the calcium levels in your blood. If you have low blood calcium before you start receiving Boncresa, it may get worse during treatment. Your low blood calcium must be treated before you receive Boncresa. Talk to your doctor before starting Boncresa. Your doctor may prescribe calcium and vitamin D to help prevent low calcium levels in your blood while you take Boncresa. Take calcium and vitamin D as your doctor tells you to.
  If you have advanced chronic kidney disease (may or may not be on kidney dialysis), Boncresa may increase your risk for severe low calcium levels in your blood, which could result in hospitalization, life-threatening events and death. A mineral and bone disorder associated with kidney disease called chronic kidney disease-mineral bone disorder (CKD-MBD) may increase your risk for severe low calcium levels in blood. Before you start Boncresa and during treatment, your doctor may need to do certain blood tests to check for CKD-MBD.
  Most people with low blood calcium levels do not have symptoms, but some people may have symptoms. Call your doctor right away if you have symptoms of low blood calcium such as:
- spasms, twitches, or cramps in your muscles
- numbness or tingling in your fingers, toes, or around your mouth
- Serious allergic reactions. Serious allergic reactions have happened in people who take denosumab products. Call your doctor or go to your nearest emergency room right away if you have any symptoms of a serious allergic reaction. Symptoms of a serious allergic reaction may include:
  - low blood pressure (hypotension)
  - rash
  - trouble breathing
  - itching
  - throat tightness
  - hives
  - swelling of your face, lips, or tongue
- Severe jaw bone problems (osteonecrosis). Severe jaw bone problems may happen when you take Boncresa. Your doctor should examine your mouth before you start Boncresa. Your doctor may tell you to see your dentist before you start Boncresa. It is important for you to practice good mouth care during treatment with Boncresa. Ask your doctor or dentist about good mouth care if you have any questions.
- Unusual thigh bone fractures. Some people have developed unusual fractures in their thigh bone. Symptoms of a fracture include new or unusual pain in your hip, groin, or thigh.
- Increased risk of broken bones, including broken bones in the spine, after stopping, skipping or delaying Boncresa. Talk with your doctor before starting Boncresa treatment. After your treatment with Boncresa is stopped, or if you skip or delay taking a dose, your risk for breaking bones, including bones in your spine, is increased. Your risk for having more than 1 broken bone in your spine is increased if you have already had a broken bone in your spine. Do not stop, skip or delay taking Boncresa without first talking with your doctor. If your Boncresa treatment is stopped, talk to your doctor about other medicine that you can take.
- Serious infections. Serious infections in your skin, lower stomach area (abdomen), bladder, or ear may happen if you take Boncresa. Inflammation of the inner lining of the heart (endocarditis) due to an infection also may happen more often in people who take Boncresa. You may need to go to the hospital for treatment if you develop an infection.
  Boncresa is a medicine that may affect the ability of your body to fight infections. People who have a weakened immune system or take medicines that affect the immune system may have an increased risk for developing serious infections. Call your doctor right away if you have any of the following symptoms of infection:
- fever or chills
- skin that looks red or swollen and is hot or tender to touch
- fever, shortness of breath, cough that will not go away
- severe abdominal pain
- frequent or urgent need to urinate or burning feeling when you urinate
- Skin problems. Skin problems such as inflammation of your skin (dermatitis), rash, and eczema may happen if you take Boncresa. Call your doctor if you have any of the following symptoms of skin problems that do not go away or get worse:
  - redness
  - your skin is dry or feels like leather
  - itching
  - blisters that ooze or become crusty
  - small bumps or patches (rash)
  - skin peeling
- Bone, joint, or muscle pain. Some people who take denosumab products develop severe bone, joint, or muscle pain.

Call your doctor right away if you have any of these side effects.

What is Boncresa?

Boncresa is a prescription medicine used to:

- Treat osteoporosis (thinning and weakening of bone) in women after menopause (“change of life”) who:
  - are at high risk for fracture (broken bone)
  - cannot use another osteoporosis medicine or other osteoporosis medicines did not work well
- Increase bone mass in men with osteoporosis who are at high risk for fracture.
- Treat osteoporosis in men and women who will be taking corticosteroid medicines (such as prednisone) for at least 6 months and are at high risk for fracture.
- Treat bone loss in men who are at high risk for fracture receiving certain treatments for prostate cancer that has not spread to other parts of the body.
- Treat bone loss in women who are at high risk for fracture receiving certain treatments for breast cancer that has not spread to other parts of the body.

It is not known if Boncresa is safe and effective in children. Boncresa is not approved for use in children.

Do not take Boncresa if you:

- have been told by your doctor that your blood calcium level is too low.
- are pregnant or plan to become pregnant.
- are allergic to denosumab products or any of the ingredients in Boncresa. See the end of this Medication Guide for a complete list of ingredients in Boncresa.

Before taking Boncresa, tell your doctor about all of your medical conditions, including if you:

- are taking other denosumab products.
- have low blood calcium.
- cannot take daily calcium and vitamin D.
- had parathyroid or thyroid surgery (glands located in your neck).
- have been told you have trouble absorbing minerals in your stomach or intestines (malabsorption syndrome).
- have kidney problems or are on kidney dialysis.
- are taking medicine that can lower your blood calcium levels.
- plan to have dental surgery or teeth removed.
- are pregnant or plan to become pregnant. Boncresa may harm your unborn baby.

Females who are able to become pregnant:

- Your healthcare provider should do a pregnancy test before you start treatment with Boncresa.
- You should use an effective method of birth control (contraception) during treatment with Boncresa and for at least 5 months after your last dose of Boncresa.
- Tell your doctor right away if you become pregnant while taking Boncresa.

- are breastfeeding or plan to breastfeed. It is not known if Boncresa passes into your breast milk. You and your doctor should decide if you will take Boncresa or breastfeed. You should not do both.

Tell your doctor about all the medicines you take, including prescription and over-the-counter medicines, vitamins, and herbal supplements.

Know the medicines you take. Keep a list of medicines with you to show to your doctor or pharmacist when you get a new medicine.

How will I receive Boncresa?

- Boncresa is an injection that will be given to you by a healthcare provider. Boncresa is injected under your skin (subcutaneous).
- You will receive Boncresa 1 time every 6 months.
- You should take calcium and vitamin D as your doctor tells you to while you receive Boncresa.
- If you miss a dose of Boncresa, you should receive your injection as soon as you can.
- Take good care of your teeth and gums while you receive Boncresa. Brush and floss your teeth regularly.
- Tell your dentist that you are receiving Boncresa before you have dental work.

What are the possible side effects of Boncresa?

Boncresa may cause serious side effects.

- See “What is the most important information I should know about Boncresa?”
- It is not known if the use of Boncresa over a long period of time may cause slow healing of broken bones.

The most common side effects of Boncresa in women who are being treated for osteoporosis after menopause are:

- back pain
- muscle pain
- pain in your arms and legs
- bladder infection
- high cholesterol

The most common side effects of Boncresain men with osteoporosis are:

- back pain
- common cold (runny nose or sore throat)
- joint pain

The most common side effects of Boncresa in patients with glucocorticoid-induced osteoporosis are:

- back pain
- lung infection (bronchitis)
- high blood pressure
- headache

The most common side effects of Boncresa in patients receiving certain treatments for prostate or breast cancer are:

- joint pain
- pain in your arms and legs
- back pain
- muscle pain

Tell your doctor if you have any side effect that bothers you or that does not go away.

These are not all the possible side effects of Boncresa.

Call your doctor for medical advice about side effects. You may report side effects to FDA at 1-800-FDA-1088.

How should I store Boncresa if I need to pick it up from a pharmacy?

- Keep Boncresa in a refrigerator at 36°F to 46°F (2°C to 8°C) in the original carton.
- Do not freeze Boncresa.
- When you remove Boncresa from the refrigerator, Boncresa must be kept at room temperature [up to 77°F (25°C)] in the original carton and must be used within 14 days.
- Do not keep Boncresa at temperatures above 77°F (25°C). Warm temperatures will affect how Boncresa works.
- Do not shake Boncresa.
- Keep Boncresa in the original carton to protect from light.

Keep Boncresa and all medicines out of the reach of children.

General information about the safe and effective use of Boncresa.

Medicines are sometimes prescribed for purposes other than those listed in a Medication Guide. Do not use Boncresa for a condition for which it was not prescribed. Do not give Boncresa to other people, even if they have the same symptoms that you have. It may harm them. You can ask your doctor or pharmacist for information about Boncresa that is written for healthcare providers.

What are the ingredients in Boncresa?

Active ingredient: denosumab-mobz

Inactive ingredients: glacial acetic acid, polysorbate 20, sorbitol, Water for Injection (USP), and sodium hydroxide

Manufactured by:

Amneal Pharmaceuticals LLC

Piscataway, NJ 08854

Product of Spain

US License No. 2241

For more information, go to www.amneal.com or call Amneal Pharmaceuticals LLC at 1-877-835-5472.

This Medication Guide has been approved by the U.S. Food and Drug Administration. Revised: 12-2025-00